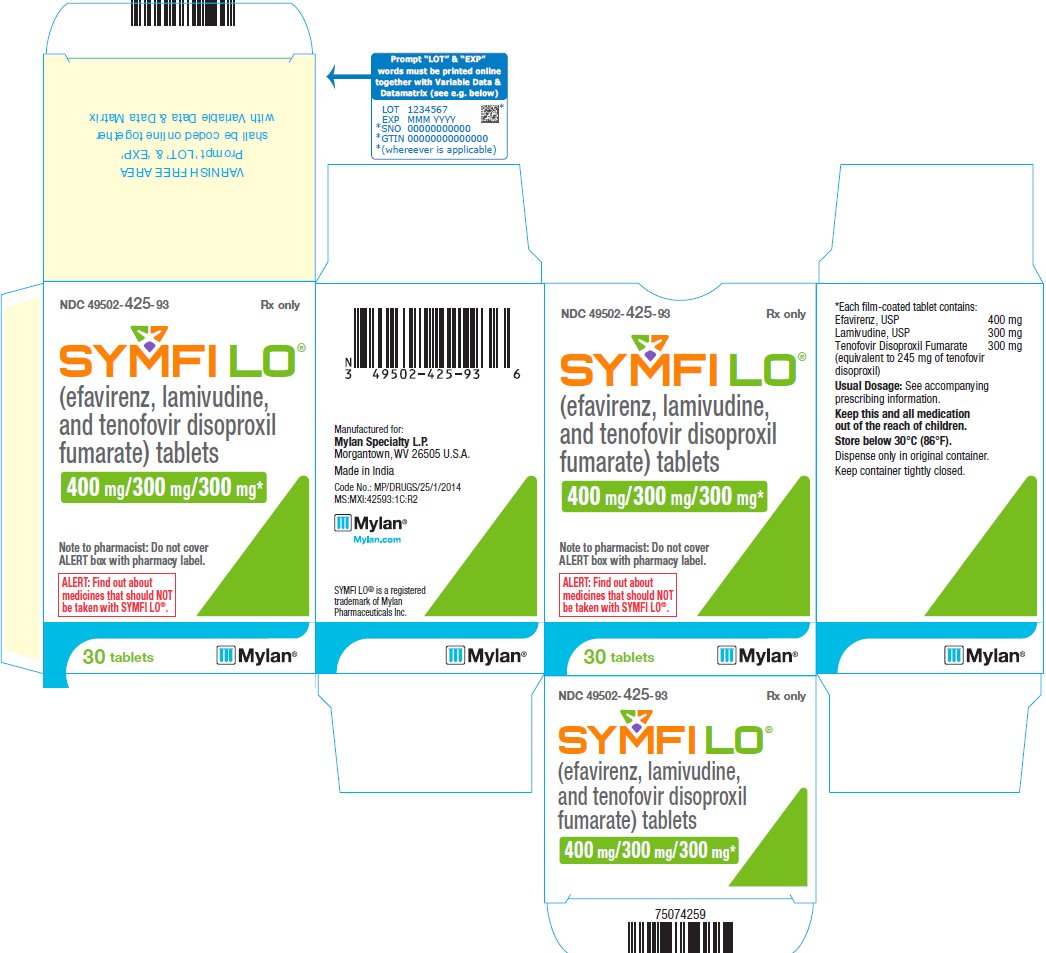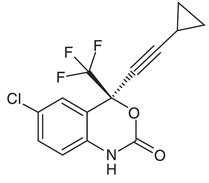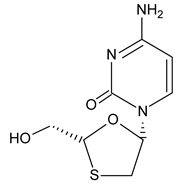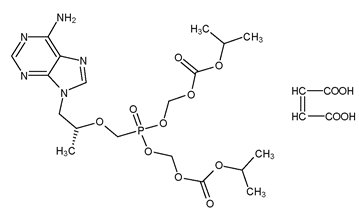 DRUG LABEL: SYMFI LO
NDC: 49502-425 | Form: TABLET, FILM COATED
Manufacturer: Viatris Specialty LLC
Category: prescription | Type: HUMAN PRESCRIPTION DRUG LABEL
Date: 20191015

ACTIVE INGREDIENTS: EFAVIRENZ 400 mg/1 1; LAMIVUDINE 300 mg/1 1; TENOFOVIR DISOPROXIL FUMARATE 300 mg/1 1
INACTIVE INGREDIENTS: CROSCARMELLOSE SODIUM; HYDROXYPROPYL CELLULOSE, UNSPECIFIED; LACTOSE MONOHYDRATE; MAGNESIUM STEARATE; MICROCRYSTALLINE CELLULOSE; POLYETHYLENE GLYCOL, UNSPECIFIED; POLYVINYL ALCOHOL, UNSPECIFIED; SODIUM LAURYL SULFATE; TALC; TITANIUM DIOXIDE; FERRIC OXIDE YELLOW

HIGHLIGHTS OF PRESCRIBING INFORMATION

These highlights do not include all the information needed to use SYMFI LO safely and effectively. See full prescribing information for SYMFI LO.
SYMFI LO®(efavirenz, lamivudine and tenofovir disoproxil fumarate) tablets, for oral use
Initial U.S. Approval: 2018

RECENT MAJOR CHANGES

Warnings and Precautions (5.1, 5.2, 5.3, 5.4, 5.6, 5.13, 5.14) 10/2019

Warnings and Precautions, Use with Interferon- and Ribavirin-Based Regimens (previous 5.10) Removed 10/2019

WARNING: POST TREATMENT ACUTE EXACERBATIONS OF HEPATITIS B

See full prescribing information for complete boxed warning.

- Severe acute exacerbations of hepatitis B have been reported in patients who are co-infected with HBV and human immunodeficiency virus (HIV-1) and have discontinued lamivudine and tenofovir disoproxil fumarate. Monitor hepatic function closely in these patients and, if appropriate, initiate anti-hepatitis B treatment. (5.1)

1 INDICATIONS AND USAGE

SYMFI LO is a three-drug combination of efavirenz (EFV), a non-nucleoside reverse transcriptase inhibitor, and lamivudine (3TC) and tenofovir disoproxil fumarate (TDF), both nucleo(t)side reverse transcriptase inhibitors and is indicated as a complete regimen for the treatment of human immunodeficiency virus type 1 (HIV-1) infection in adult and pediatric patients weighing at least 35 kg. (1)

2 DOSAGE AND ADMINISTRATION

- Testing: Prior to initiation and during treatment with SYMFI LO, patients should be tested for hepatitis B virus infection, and estimated creatinine clearance, urine glucose, and urine protein should be obtained. (2.1)
- Recommended dose: One tablet taken orally once daily on an empty stomach, preferably at bedtime. (2.2)
- Renal Impairment: Not recommended in patients with CrCL less than 50 mL/min or patients with end-stage renal disease requiring hemodialysis. (2.3)
- Hepatic Impairment: Not recommended for patients with moderate or severe hepatic impairment. Use caution in patients with mild hepatic impairment. (2.4)

3 DOSAGE FORMS AND STRENGTHS

Tablets: 400 mg efavirenz, 300 mg lamivudine and 300 mg tenofovir disoproxil fumarate (equivalent to 245 mg of tenofovir disoproxil). (3)

4 CONTRAINDICATIONS

- SYMFI LO is contraindicated in patients with previous hypersensitivity (e.g., Stevens-Johnson syndrome, erythema multiforme, or toxic skin eruptions) to any of the components of this product. (4)
- Coadministration with elbasvir/grazoprevir. (4)

5 WARNINGS AND PRECAUTIONS

- Lactic Acidosis/Severe Hepatomegaly with Steatosis: Discontinue treatment in patients who develop symptoms or laboratory findings suggestive of lactic acidosis or pronounced hepatotoxicity. (5.2)
- New Onset or Worsening Renal Impairment: Can include acute renal failure and Fanconi syndrome. Avoid administering SYMFI LO with concurrent or recent use of nephrotoxic drugs. (5.4)
- Serious Psychiatric Symptoms: Immediate medical evaluation is recommended for serious psychiatric symptoms such as severe depression or suicidal ideation. (5.5)
- Nervous System Symptoms (NSS): NSS are frequent, usually begin 1 to 2 days after initiating therapy and resolve in 2 to 4 weeks. Dosing at bedtime may improve tolerability. NSS are not predictive of onset of psychiatric symptoms. (5.6)
- Rash: Rash usually begins within 1 to 2 weeks after initiating therapy and resolves within 4 weeks. Discontinue if severe rash develops. (5.8)
- Hepatotoxicity: Monitor liver function tests before and during treatment in patients with underlying hepatic disease, including hepatitis B or C coinfection, marked transaminase elevations, or who are taking medications associated with liver toxicity. Among reported cases of hepatic failure, a few occurred in patients with no pre-existing hepatic disease. (5.9, 8.7)
- Pancreatitis: Use with caution in pediatric patients with a history of pancreatitis or other significant risk factors for pancreatitis. Discontinue SYMFI LO as clinically appropriate. (5.10)
- Convulsions: Use caution in patients with a history of seizures. (5.11)
- Lipids: Total cholesterol and triglyceride elevations. Monitor before therapy and periodically thereafter. (5.12)
- Decreases in Bone Mineral Density (BMD): Observed in HIV-infected patients. Consider assessment of BMD in patients with a history of pathologic fracture or other risk factors for osteoporosis or bone loss. (5.13)
- Immune Reconstitution Syndrome: Observed in HIV-infected patients. May necessitate further evaluation and treatment. (5.14)
- Redistribution/Accumulation of Body Fat: Observed in HIV-infected patients receiving antiretroviral combination therapy. (5.15)

6 ADVERSE REACTIONS

- Most common adverse reactions (> 5% with SYMFI LO) are rash and dizziness. (6)

To report SUSPECTED ADVERSE REACTIONS, contact Mylan at 1-877-446-3679 (1-877-4-INFO-RX) or FDA at 1-800-FDA-1088 or www.fda.gov/medwatch.

7 DRUG INTERACTIONS

- SYMFI LO should not be administered with other antiretroviral medications for the treatment of HIV-1 infection. (7.1)
- Coadministration of SYMFI LO can alter the concentrations of other drugs and other drugs may alter the concentration of SYMFI LO. The potential for drug-drug interactions should be considered before and during therapy. (5.3, 7)

8 USE IN SPECIFIC POPULATIONS

- Pregnancy: Women should avoid pregnancy during EFV therapy, a component of SYMFI LO, and for 12 weeks after discontinuation. (5.7, 8.1, 8.3)
- Lactation: Breastfeeding not recommended due to potential for HIV transmission. (8.2)
- Females and Males of Reproductive Potential: Pregnancy testing and contraception are recommended. (8.3)

FULL PRESCRIBING INFORMATION

WARNING: POST TREATMENT ACUTE EXACERBATIONS OF HEPATITIS B

Severe acute exacerbations of hepatitis B have been reported in patients who are co-infected with hepatitis B virus (HBV) and human immunodeficiency virus (HIV-1) and have discontinued lamivudine or tenofovir disoproxil fumarate, two components of SYMFI LO. Monitor hepatic function closely in these patients and, if appropriate, initiate anti-hepatitis B treatment [see Warnings and Precautions (5.1)].

1 INDICATIONS AND USAGE

SYMFI LO® (efavirenz, lamivudine and tenofovir disoproxil fumarate) is indicated as a complete regimen for the treatment of human immunodeficiency virus type 1 (HIV-1) infection in adult and pediatric patients weighing at least 35 kg.

2 DOSAGE AND ADMINISTRATION

2.1 Testing Prior to Initiation and During Treatment with SYMFI LO

Prior to initiation of SYMFI LO, test patients for hepatitis B virus infection [see Warnings and Precautions (5.1)].

It is recommended that serum creatinine, serum phosphorus, estimated creatinine clearance, urine glucose, and urine protein be assessed before initiating SYMFI LO and during therapy in all patients as clinically appropriate [see Warnings and Precautions (5.4)].

Monitor hepatic function prior to and during treatment with SYMFI LO [see Warnings and Precautions (5.9)].

2.2 Recommended Dosage for Adult and Pediatric Patients Weighing at Least 35 kg

SYMFI LO is a three-drug fixed-dose combination product containing 400 mg of efavirenz (EFV), 300 mg of lamivudine (3TC), and 300 mg of tenofovir disoproxil fumarate (TDF). The recommended dosage of SYMFI LO in HIV-1-infected adults and pediatric patients weighing at least 35 kg is one tablet taken orally once daily. SYMFI LO tablets should be taken on an empty stomach, preferably at bedtime. Dosing at bedtime may improve the tolerability of nervous system symptoms [see Warnings and Precautions (5.6) and Adverse Reactions (6.1)].

2.3 Not Recommended in Renal Impairment

Because SYMFI LO is a fixed-dose combination tablet and cannot be dose adjusted, it is not recommended for patients with impaired renal function (creatinine clearance less than 50 mL/min) or patients with end-stage renal disease (ESRD) requiring hemodialysis [see Use in Specific Populations (8.6)].

2.4 Not Recommended in Moderate to Severe Hepatic Impairment

SYMFI LO is not recommended in patients with moderate or severe hepatic impairment (Child-Pugh B or C) [see Warnings and Precautions (5.9) and Use in Specific Populations (8.7)].

3 DOSAGE FORMS AND STRENGTHS

Tablets: 400 mg of efavirenz, 300 mg of lamivudine, and 300 mg of tenofovir disoproxil fumarate (equivalent to 245 mg of tenofovir disoproxil).

The 400 mg/300 mg/300 mg tablets are white to off-white, film-coated, oval, unscored tablets debossed with “M” on one side and “TLE” on the other side.

4 CONTRAINDICATIONS

SYMFI LO is contraindicated:

- in patients with a previous hypersensitivity reaction (e.g., Stevens-Johnson syndrome, erythema multiforme, or toxic skin eruptions) to any of the components contained in the formulation [see Warnings and Precautions (5.8)].
- when coadministered with elbasvir and grazoprevir [see Warnings and Precautions (5.3) and Drug Interactions (7.5)].

5 WARNINGS AND PRECAUTIONS

5.1 Severe Acute Exacerbation of Hepatitis B in Patients Coinfected with HIV-1 and HBV

Posttreatment Exacerbations of Hepatitis

All patients with HIV-1 should be tested for the presence of chronic hepatitis B virus (HBV) before initiating antiretroviral therapy [see Dosage and Administration (2.1)]. Discontinuation of anti-HBV therapy, including 3TC and TDF, may be associated with severe acute exacerbations of hepatitis B. Patients infected with HBV who discontinue SYMFI LO should be closely monitored with both clinical and laboratory follow-up for at least several months after stopping treatment. If appropriate, resumption of anti-hepatitis B therapy may be warranted.

Important Differences Among Lamivudine-Containing Products

SYMFI LO tablets contain a higher dose of the same active ingredient, 3TC, than EPIVIR-HBV® tablets. EPIVIR-HBV was developed for patients with chronic hepatitis B. The formulation and dosage of 3TC in EPIVIR-HBV are not appropriate for patients co-infected with HIV-1 and HBV. Safety and efficacy of 3TC have not been established for treatment of chronic hepatitis B in patients co-infected with HIV-1 and HBV.

If treatment with EPIVIR-HBV, TDF, or a tenofovir alafenamide (TAF)-containing product is prescribed for chronic hepatitis B for a patient with unrecognized or untreated HIV-1 infection, rapid emergence of HIV-1 resistance is likely to result because of the subtherapeutic dose and the inappropriateness of monotherapy HIV-1 treatment.

5.2 Lactic Acidosis and Severe Hepatomegaly with Steatosis

Lactic acidosis and severe hepatomegaly with steatosis, including fatal cases, have been reported with the use of nucleoside analogs and other antiretrovirals. Female sex and obesity may be risk factors for the development of lactic acidosis and severe hepatomegaly with steatosis in patients treated with antiretroviral nucleoside analogues. Treatment should be suspended in any patient who develops clinical or laboratory findings suggestive of lactic acidosis or pronounced hepatotoxicity, which may include hepatomegaly and steatosis even in the absence of marked transaminase elevations.

5.3 Risk of Adverse Reactions or Loss of Virologic Response Due to Drug Interactions

The concomitant use of SYMFI LO and other drugs may result in known or potentially significant drug interactions, some of which may lead to [see Contraindications (4) and Drug Interactions (7.5)]:

- Loss of therapeutic effect of SYMFI LO and possible development of resistance.
- Possible clinically significant adverse reactions from greater exposures of concomitant drugs.

See Table 5 for steps to prevent or manage these possible and known significant drug interactions, including dosing recommendations. Consider the potential for drug interactions prior to and during therapy with SYMFI LO; review concomitant medications during therapy with SYMFI LO; and monitor for the adverse reactions associated with the concomitant drugs.

5.4 New Onset or Worsening Renal Impairment

TDF, a component of SYMFI LO is principally eliminated by the kidney. Renal impairment, including cases of acute renal failure and Fanconi syndrome (renal tubular injury with severe hypophosphatemia), has been reported with the use of TDF [see Adverse Reactions (6.2)].

Prior to initiation and during use of SYMFI LO, on a clinically appropriate schedule, assess serum creatinine, estimated creatinine clearance, urine glucose, and urine protein in all patients.

Avoid SYMFI LO with concurrent or recent use of a nephrotoxic agent (e.g., high-dose or multiple non-steroidal anti-inflammatory drugs [NSAIDs]) [see Drug Interactions (7.3)]. Cases of acute renal failure after initiation of high-dose or multiple NSAIDs have been reported in HIV-infected patients with risk factors for renal dysfunction who appeared stable on TDF. Some patients required hospitalization and renal replacement therapy. Alternatives to NSAIDs should be considered, if needed, in patients at risk for renal dysfunction.

Persistent or worsening bone pain, pain in extremities, fractures and/or muscular pain or weakness may be manifestations of proximal renal tubulopathy and should prompt an evaluation of renal function in patients at risk of renal dysfunction.

5.5 Psychiatric Symptoms

Serious psychiatric adverse experiences have been reported in patients treated with EFV, a component of SYMFI LO. In controlled trials of 1008 patients treated with regimens containing EFV for a mean of 2.1 years and 635 patients treated with control regimens for a mean of 1.5 years, the frequency (regardless of causality) of specific serious psychiatric events among patients who received EFV or control regimens, respectively, were severe depression (2.4%, 0.9%), suicidal ideation (0.7%, 0.3%), nonfatal suicide attempts (0.5%, 0), aggressive behavior (0.4%, 0.5%), paranoid reactions (0.4%, 0.3%), and manic reactions (0.2%, 0.3%). When psychiatric symptoms similar to those noted above were combined and evaluated as a group in a multifactorial analysis of data from a study using EFV 600 mg, treatment with EFV was associated with an increase in the occurrence of these selected psychiatric symptoms. Other factors associated with an increase in the occurrence of these psychiatric symptoms were history of injection drug use, psychiatric history, and receipt of psychiatric medication at study entry; similar associations were observed in both the EFV and control treatment groups. In a study using EFV 600 mg, onset of new serious psychiatric symptoms occurred throughout the study for both EFV-treated and control-treated patients. One percent of EFV-treated patients discontinued or interrupted treatment because of one or more of these selected psychiatric symptoms.

In the ENCORE1 (Evaluation of Novel Concepts in Optimization of antiRetroviral Efficacy) study, at Week 48 the frequency (regardless of causality) of the most common (occurring in > 1% patients) psychiatric events among patients who received EFV 400 mg (N = 321) or EFV 600 mg (N = 309) regimens, respectively, were: abnormal dreams (8.7%, 11.3%), insomnia (6.2%, 6.5%), somnolence (3.1%, 3.9%), depression (3.1%, 1.6%), nightmare (1.9%, 2.6%), sleep disorder (2.2%, 1.3%), and anxiety (1.2%, 1.3%).

There have also been occasional postmarketing reports of death by suicide, delusions, psychosis-like behavior, although a causal relationship to the use of EFV cannot be determined from these reports [see Adverse Reactions (6.2)]. Postmarketing cases of catatonia have also been reported and may be associated with increased efavirenz exposure. Patients with serious psychiatric adverse experiences should seek immediate medical evaluation to assess the possibility that the symptoms may be related to the use of EFV, and if so, to determine whether the risks of continued therapy outweigh the benefits.

5.6 Nervous System Symptoms

Fifty-three percent (531/1008) of patients receiving EFV, a component of SYMFI LO, in controlled trials reported central nervous system symptoms (any grade, regardless of causality) compared to 25% (156/635) of patients receiving control regimens. These symptoms included, but were not limited to, dizziness (28.1% of the 1008 patients), insomnia (16.3%), impaired concentration (8.3%), somnolence (7.0%), abnormal dreams (6.2%), and hallucinations (1.2%). These symptoms were severe in 2.0% of patients and 2.1% of patients discontinued therapy as a result. These symptoms usually begin during the first or second day of therapy and generally resolve after the first 2 to 4 weeks of therapy. After 4 weeks of therapy, the prevalence of nervous system symptoms of at least moderate severity ranged from 5% to 9% in patients treated with regimens containing EFV and from 3% to 5% in patients treated with a control regimen. Inform patients that these common symptoms were likely to improve with continued therapy and were not predictive of subsequent onset of the less frequent psychiatric symptoms [see Warnings and Precautions (5.5)]. Dosing at bedtime may improve the tolerability of these nervous system symptoms [see Dosage and Administration (2.2)].

In the ENCORE1 study, at Week 48, 40% of EFV 400 mg recipients and 48% of EFV 600 mg recipients reported central nervous system disorders. The most common symptoms (> 10%) were dizziness (27% vs. 35%) and headache (11% vs. 11%).

Late-onset neurotoxicity, including ataxia and encephalopathy (impaired consciousness, confusion, psychomotor slowing, psychosis, delirium), may occur months to years after beginning efavirenz therapy. Some events of late-onset neurotoxicity have occurred in patients with CYP2B6 genetic polymorphisms which are associated with increased efavirenz levels despite daily dosages of 600 mg of efavirenz. Patients presenting with signs and symptoms of serious neurologic adverse experiences should be evaluated promptly to assess the possibility that these events may be related to efavirenz use, and whether discontinuation of SYMFI LO is warranted.

5.7 Embryo-Fetal Toxicity

EFV, a component of SYMFI LO, may cause fetal harm when administered during the first trimester to a pregnant woman. Advise females of reproductive potential who are receiving EFV to avoid pregnancy [see Use in Specific Populations (8.1, 8.3)].

5.8 Skin and Systemic Hypersensitivity Reaction

In controlled clinical trials, 26% (266/1008) of patients treated with 600 mg EFV experienced new-onset skin rash compared with 17% (111/635) of patients treated in control groups. Rash associated with blistering, moist desquamation, or ulceration occurred in 0.9% (9/1008) of patients treated with EFV. The incidence of Grade 4 rash (e.g., erythema multiforme, Stevens-Johnson syndrome) in patients treated with EFV in all studies and expanded access was 0.1%. Rashes are usually mild-to-moderate maculopapular skin eruptions that occur within the first 2 weeks of initiating therapy with EFV (median time to onset of rash in adults was 11 days) and, in most patients continuing therapy with EFV, rash resolves within 1 month (median duration, 16 days). The discontinuation rate for rash in clinical trials was 1.7% (17/1008).

EFV can generally be reinitiated in patients interrupting therapy because of rash. EFV should be discontinued in patients developing severe rash associated with blistering, desquamation, mucosal involvement, or fever. Appropriate antihistamines and/or corticosteroids may improve the tolerability and hasten the resolution of rash. For patients who have had a life-threatening cutaneous reaction (e.g., Stevens-Johnson syndrome), alternate therapy should be considered [see Contraindications (4)].

In the ENCORE1 study at Week 48, different types of rash (such as rash, rash papular, rash maculopapular and rash pruritic) occurred in 32% of EFV 600 mg recipients and 26% of EFV 400 mg recipients. Grade 3-4 rash was reported in 3% of EFV 600 mg recipients and 1% of EFV 400 mg recipients. The discontinuation rate for rash in the ENCORE1 study was 3% of EFV 600 mg recipients and 1% of EFV 400 mg recipients.

5.9 Hepatotoxicity

Postmarketing cases of hepatitis, including fulminant hepatitis progressing to liver failure requiring transplantation or resulting in death, have been reported in patients treated with EFV. Reports have included patients with underlying hepatic disease, including coinfection with hepatitis B or C, and patients without pre-existing hepatic disease or other identifiable risk factors.

EFV, a component of SYMFI LO, is not recommended for patients with moderate or severe hepatic impairment. Careful monitoring is recommended for patients with mild hepatic impairment receiving EFV [see Adverse Reactions (6.1) and Use in Specific Populations (8.7)].

Monitoring of liver enzymes before and during treatment is recommended for all patients [see Dosage and Administration (2.1)]. Consider discontinuing SYMFI LO in patients with persistent elevations of serum transaminases to greater than five times the upper limit of the normal range.

Discontinue SYMFI LO if elevation of serum transaminases is accompanied by clinical signs or symptoms of hepatitis or hepatic decompensation.

5.10 Pancreatitis

In pediatric patients with a history of prior antiretroviral nucleoside exposure, a history of pancreatitis, or other significant risk factors for the development of pancreatitis, 3TC, a component of SYMFI LO, should be used with caution. Treatment with SYMFI LO should be stopped immediately if clinical signs, symptoms, or laboratory abnormalities suggestive of pancreatitis occur [see Adverse Reactions (6.1)].

5.11 Convulsions

Convulsions have been observed in patients receiving EFV, generally in the presence of known medical history of seizures [see Nonclinical Toxicology (13.2)]. Caution should be taken in any patient with a history of seizures. Patients who are receiving concomitant anticonvulsant medications primarily metabolized by the liver, such as phenytoin and phenobarbital, may require periodic monitoring of plasma levels [see Drug Interactions (7.5)].

5.12 Lipid Elevations

Treatment with EFV has resulted in increases in the concentration of total cholesterol and triglycerides. Cholesterol and triglyceride testing should be performed before initiating EFV therapy and at periodic intervals during therapy.

5.13 Bone Loss and Mineralization Effects

Bone Mineral Density (BMD)

In clinical trials in HIV-1-infected adults, TDF was associated with slightly greater decreases in BMD and increases in biochemical markers of bone metabolism, suggesting increased bone turnover relative to comparators [see Adverse Reactions (6.1)]. Serum parathyroid hormone levels and 1,25 Vitamin D levels were also higher in subjects receiving TDF.

The effects of TDF-associated changes in BMD and biochemical markers on long-term bone health and future fracture risk in adults and pediatric subjects 2 years and older are unknown. The long-term effect of lower spine and total body BMD on skeletal growth in pediatric patients, and in particular, the effects of long-duration exposuire in younger children is unknown.

Although the effect of supplementation with calcium and vitamin D was not studied, such supplementation may be beneficial. Assessment of BMD should be considered for adult and pediatric patients who have a history of pathologic bone fracture or other risk factors for osteoporosis or bone loss. If bone abnormalities are suspected then appropriate consultation should be obtained.

Mineralization Defects

Cases of osteomalacia associated with proximal renal tubulopathy, manifested as bone pain or pain in extremities and which may contribute to fractures, have been reported in association with TDF use [see Adverse Reactions (6.2)]. Arthralgia and muscle pain or weakness have also been reported in cases of proximal renal tubulopathy. Hypophosphatemia and osteomalacia secondary to proximal renal tubulopathy should be considered in patients at risk of renal dysfunction who present with persistent or worsening bone or muscle symptoms while receiving TDF-containing products [see Warnings and Precautions (5.4)].

5.14 Immune Reconstitution Syndrome

Immune reconstitution syndrome has been reported in HIV-infected patients treated with combination antiretroviral therapy, including EFV, 3TC, and TDF. During the initial phase of combination antiretroviral treatment, patients whose immune system responds may develop an inflammatory response to indolent or residual opportunistic infections (such as Mycobacterium avium infection, cytomegalovirus, Pneumocystis jirovecii pneumonia [PCP], or tuberculosis), which may necessitate further evaluation and treatment.

Autoimmune disorders (such as Graves’ disease, polymyositis, Guillain-Barre syndrome, and autoimmune hepatitis) have also been reported to occur in the setting of immune reconstitution; however, the time to onset is more variable, and can occur many months after initiation of treatment.

5.15 Fat Redistribution

In HIV-infected patients, redistribution/accumulation of body fat including central obesity, dorsocervical fat enlargement (buffalo hump), peripheral wasting, facial wasting, breast enlargement, and “cushingoid appearance” have been observed in patients receiving combination antiretroviral therapy. The mechanism and long-term consequences of these events are currently unknown. A causal relationship has not been established.

5.16 QTc Prolongation

QTc prolongation has been observed with the use of EFV [see Drug Interactions (7.2, 7.5) and Clinical Pharmacology (12.2)]. Consider alternatives to products containing EFV when coadministered with a drug with a known risk of Torsade de Pointes or when administered to patients at higher risk of Torsade de Pointes.

6 ADVERSE REACTIONS

The following adverse reactions are discussed in other sections of the labeling:

- Exacerbations of Hepatitis B [see Boxed Warning, Warnings and Precautions (5.1)].
- Lactic Acidosis/Severe Hepatomegaly with Steatosis [see Warnings and Precautions (5.2)].
- New Onset or Worsening Renal Impairment [see Warnings and Precautions (5.4)].
- Psychiatric Symptoms [see Warnings and Precautions (5.5)].
- Nervous System Symptoms [see Warnings and Precautions (5.6)].
- Skin and Systemic Hypersensitivity Reaction [see Warnings and Precautions (5.8)].
- Hepatotoxicity [see Warnings and Precautions (5.9)].
- Pancreatitis [see Warnings and Precautions (5.10)].
- Bone Loss and Mineralization Effects [see Warnings and Precautions (5.13)].
- Immune Reconstitution Syndrome [see Warnings and Precautions (5.14)].
- Fat Redistribution [see Warnings and Precautions (5.15)].

6.1 Clinical Trials Experience

Because clinical studies are conducted under widely varying conditions, the adverse reaction rates observed in clinical trials of a drug cannot be directly compared to rates in the clinical trials of another drug and may not reflect the rates observed in practice.

Efavirenz, Lamivudine and Tenofovir Disoproxil Fumarate

Clinical Trials in Treatment-Naïve HIV-1 Infected Adult Subjects

In Trial 903, 600 antiretroviral-naïve subjects received TDF (N = 299) or stavudine (d4T) (N = 301) administered in combination with 3TC and EFV for 144 weeks. The most common adverse reactions were mild to moderate gastrointestinal events and dizziness. Mild adverse reactions (Grade 1) were common with a similar incidence in both arms and included dizziness, diarrhea, and nausea. Table 1 provides the treatment-emergent adverse reactions (Grades 2-4) occurring in greater than or equal to 5% of subjects treated in any treatment group.

Table 1. Selected Adverse Reactions [Frequencies of adverse reactions are based on all treatment-emergent adverse events, regardless of relationship to study drug.] (Grades 2-4) Reported in ≥ 5% in Any Treatment Group in Trial 903 (0-144 Weeks)
 | TDF + 3TC + EFV | d4T + 3TC + EFV
 | N = 299 | N = 301
Rash event [Rash event includes rash, pruritus, maculopapular rash, urticaria, vesiculobullous rash, and pustular rash.] | 18% | 12%
Headache | 14% | 17%
Pain | 13% | 12%
Diarrhea | 11% | 13%
Depression | 11% | 10%
Back pain | 9% | 8%
Nausea | 8% | 9%
Fever | 8% | 7%
Abdominal pain | 7% | 12%
Asthenia | 6% | 7%
Anxiety | 6% | 6%
Vomiting | 5% | 9%
Insomnia | 5% | 8%
Arthralgia | 5% | 7%
Pneumonia | 5% | 5%
Dyspepsia | 4% | 5%
Dizziness | 3% | 6%
Myalgia | 3% | 5%
Lipodystrophy [Lipodystrophy represents a variety of investigator-described adverse events not a protocol-defined syndrome.] | 1% | 8%
Peripheral neuropathy [Peripheral neuropathy includes peripheral neuritis and neuropathy.] | 1% | 5%

ENCORE1 Study - Adverse Reactions

The most common adverse reactions seen in a double-blind comparative controlled study in which 630 treatment-naïve subjects received EFV 400 mg (N = 321) or EFV 600 mg (N = 309) in combination with fixed-dose emtricitabine (FTC)/TDF for 48 weeks were mild to moderate gastrointestinal events, dizziness, abnormal dreams, and rash. Selected clinical adverse reactions of moderate or severe intensity reported in ≥ 2% of treatment-naive patients receiving combination therapy including EFV 400 mg and EFV 600 mg are presented in Table 2.

Table 2. Selected Adverse Reactions [Frequencies of adverse reactions are based on all treatment-emergent adverse events, regardless of relationship to study drug.] (Grades 2-4) Reported in ≥ 2% in Either Treatment Group in the ENCORE1 Study through Week 48
 | EFV 400 mg + FTC/TDF | EFV 600 mg + FTC/TDF
 | N = 321 | N = 309
Rash event [Rash events include dermatitis allergic, drug hypersensitivity, pruritus generalized, eosinophilic pustular folliculitis, rash, rash erythematous, rash generalized, rash macular, rash maculopapular, rash morbilliform, rash papular, rash pruritic, rash vesicular, and urticaria.] | 9% | 13%
Dizziness | 6% | 9%
Insomnia | 3% | 4%
Abnormal dreams | 2% | 2%
Headache | 1% | 3%
Diarrhea | 2% | 3%
Vomiting | 1% | 2%
Pyrexia | 2% | 1%
Upper respiratory tract infection | 3% | 1%
Nasopharyngitis | 3% | 2%
Herpes zoster | 3% | 1%
Gastroenteritis | 2% | 2%

Laboratory Abnormalities

Table 3 provides a list of laboratory abnormalities (Grades 3-4) observed in Trial 903. With the exception of fasting cholesterol and fasting triglyceride elevations that were more common in the d4T group (40% and 9%) compared with the TDF group (19% and 1%) respectively, laboratory abnormalities observed in this trial occurred with similar frequency in the TDF and d4T treatment arms.

Table 3. Grade 3-4 Laboratory Abnormalities Reported in ≥ 1% of Patients Randomized to Efavirenz, Lamivudine and Tenofovir Disoproxil Fumarate in Study 903 (0-144 Weeks)
 | TDF + 3TC + EFV | d4T + 3TC + EFV
 | N = 299 | N = 301
Any ≥ Grade 3 Laboratory Abnormality | 36% | 42%
Fasting Cholesterol (> 240 mg/dL) | 19% | 40%
Creatine Kinase (M: > 990 U/L; F: > 845 U/L) | 12% | 12%
Serum Amylase (> 175 U/L) | 9% | 8%
AST (M: > 180 U/L; F: > 170 U/L) | 5% | 7%
ALT (M: > 215 U/L; F: > 170 U/L) | 4% | 5%
Hematuria (> 100 RBC/HPF) | 7% | 7%
Neutrophils (< 750/mm^3) | 3% | 1%
Fasting Triglycerides (> 750 mg/dL) | 1% | 9%

In ENCORE1 study, a summary of Grade 3 and 4 laboratory abnormalities is provided in Table 4.

Table 4. Grades 3-4 Laboratory Abnormalities in ≥ 2% in Either Treatment Group Through Week 48
Laboratory Parameter | EFV 400 mg + FTC + TDF | EFV 600 mg + FTC + TDF
Laboratory Parameter | N = 321 | N = 309
ALT | 5% | 3%
AST | 2% | 2%
Total bilirubin | 0.3% | 3%
Cholesterol | 2% | 5%
Neutrophils | 2% | 3%
Phosphorus | 2% | 3%

Pancreatitis

Pancreatitis, which has been fatal in some cases, has been observed in antiretroviral nucleoside-experienced pediatric subjects receiving 3TC alone or in combination with other antiretroviral agents [see Warnings and Precautions (5.10)].

Changes in Bone Mineral Density

In HIV-1-infected adult subjects in Trial 903, there was a significantly greater mean percentage decrease from baseline in BMD at the lumbar spine in subjects receiving TDF + 3TC + EFV (-2.2% ± 3.9) compared with subjects receiving d4T + 3TC + EFV (-1.0% ± 4.6) through 144 weeks. Changes in BMD at the hip were similar between the two treatment groups (-2.8% ± 3.5 in the TDF group vs. -2.4% ± 4.5 in the d4T group). In both groups, the majority of the reduction in BMD occurred in the first 24-48 weeks of the trial and this reduction was sustained through Week 144. Twenty-eight percent of TDF-treated subjects vs. 21% of the d4T-treated subjects lost at least 5% of BMD at the spine or 7% of BMD at the hip. Clinically relevant fractures (excluding fingers and toes) were reported in 4 subjects in the TDF group and 6 subjects in the d4T group. In addition, there were significant increases in biochemical markers of bone metabolism (serum bone-specific alkaline phosphatase, serum osteocalcin, serum C telopeptide, and urinary N telopeptide) and higher serum parathyroid hormone levels and 1,25 Vitamin D levels in the TDF group relative to the d4T group; however, except for bone-specific alkaline phosphatase, these changes resulted in values that remained within the normal range [see Warnings and Precautions (5.13)].

6.2 Postmarketing Experience

The following adverse reactions have been identified during post-approval use for each of the individual components of SYMFI LO (EFV, 3TC, and TDF). Because these reactions are reported voluntarily from a population of unknown size, it is not always possible to reliably estimate their frequency or establish causal relationship to drug exposure. These reactions have been chosen for inclusion due to a combination of their seriousness, frequency of reporting, or potential causal connection to EFV, 3TC, and TDF.

Efavirenz

Body as a Whole: allergic reactions, asthenia, redistribution/accumulation of body fat [see Warnings and Precautions (5.15)].

Central and Peripheral Nervous System: abnormal coordination, ataxia, encephalopathy, cerebellar coordination and balance disturbances, convulsions, hypoesthesia, paresthesia, neuropathy, tremor, vertigo.

Endocrine: gynecomastia.

Gastrointestinal: constipation, malabsorption.

Cardiovascular: flushing, palpitations.

Liver and Biliary System: hepatic enzyme increase, hepatic failure, hepatitis.

Metabolic and Nutritional: hypercholesterolemia, hypertriglyceridemia.

Musculoskeletal: arthralgia, myalgia, myopathy.

Psychiatric: aggressive reactions, agitation, delusions, emotional lability, mania, neurosis, paranoia, psychosis, suicide, catatonia.

Respiratory: dyspnea.

Skin and Appendages: erythema multiforme, photoallergic dermatitis, Stevens-Johnson syndrome.

Special Senses: abnormal vision, tinnitus.

Lamivudine

Body as a Whole: redistribution/accumulation of body fat [see Warnings and Precautions (5.15)].

Endocrine and Metabolic: hyperglycemia.

General: weakness.

Hemic and Lymphatic: anemia (including pure red cell aplasia and severe anemias progressing on therapy).

Hepatic and Pancreatic: lactic acidosis and hepatic steatosis, posttreatment exacerbation of hepatitis B [see Boxed Warning, Warnings and Precautions (5.1, 5.2)].

Hypersensitivity: anaphylaxis, urticaria.

Musculoskeletal: muscle weakness, CPK elevation, rhabdomyolysis.

Skin: Alopecia, pruritus.

Tenofovir Disoproxil Fumarate

Immune System Disorders: allergic reaction, including angioedema.

Metabolism and Nutrition Disorders: lactic acidosis, hypokalemia, hypophosphatemia.

Respiratory, Thoracic, and Mediastinal Disorders: dyspnea.

Gastrointestinal Disorders: pancreatitis, increased amylase, abdominal pain.

Renal and Urinary Disorders: renal insufficiency, acute renal failure, renal failure, acute tubular necrosis, Fanconi syndrome, proximal renal tubulopathy, interstitial nephritis (including acute cases), nephrogenic diabetes insipidus, renal insufficiency, increased creatinine, proteinuria, polyuria [see Warnings and Precautions (5.4)].

Hepatobiliary Disorders: hepatic steatosis, hepatitis, increased liver enzymes (most commonly AST, ALT gamma GT).

Skin and Subcutaneous Tissue Disorders: rash.

Musculoskeletal and Connective Tissue Disorders: rhabdomyolysis, osteomalacia (manifested as bone pain and which may contribute to fractures), muscular weakness, myopathy.

General Disorders and Administration Site Conditions: asthenia.

The following adverse reactions, listed under the body system headings above, may occur as a consequence of proximal renal tubulopathy: rhabdomyolysis, osteomalacia, hypokalemia, muscular weakness, myopathy, hypophosphatemia.

7 DRUG INTERACTIONS

7.1 Not Recommended with Other Antiretroviral Medications

SYMFI LO is a complete regimen for the treatment of HIV-1 infection; therefore, it should not be administered with other antiretroviral medications for treatment of HIV-1 infection.

7.2 QT Prolonging Drugs

There is limited information available on the potential for a pharmacodynamic interaction between EFV and drugs that prolong the QTc interval. QTc prolongation has been observed with the use of EFV [see Clinical Pharmacology (12.2)]. Consider alternatives to EFV when coadministered with a drug with a known risk of Torsade de Pointes.

7.3 Drugs Affecting Renal Function

Tenofovir is primarily eliminated by the kidneys [see Clinical Pharmacology (12.3)]. Coadministration of EFV/3TC/TDF with drugs that are eliminated by active tubular secretion may increase concentrations of tenofovir and/or the coadministered drug. Some examples include, but are not limited to, acyclovir, cidofovir, ganciclovir, valacyclovir, valganciclovir, aminoglycosides (e.g., gentamicin), and high-dose or multiple NSAIDs [see Warnings and Precautions (5.4)]. Drugs that decrease renal function may increase concentrations of tenofovir.

7.4 Cannabinoid Test Interaction

EFV does not bind to cannabinoid receptors. False-positive urine cannabinoid test results have been reported with some screening assays in uninfected and HIV-infected subjects receiving EFV. Confirmation of positive screening tests for cannabinoids by a more specific method is recommended.

7.5 Established and Other Potentially Significant Interactions

EFV has been shown in vivo to induce CYP3A and CYP2B6. Other compounds that are substrates of CYP3A or CYP2B6 may have decreased plasma concentrations when coadministered with EFV.

Drugs that induce CYP3A activity (e.g., phenobarbital, rifampin, rifabutin) would be expected to increase the clearance of EFV resulting in lowered plasma concentrations.

No drug interaction studies have been conducted using SYMFI LO. However, drug interaction studies have been conducted with the individual components of SYMFI LO (EFV, 3TC, and TDF) [see Clinical Pharmacology (12.3)].

Drug interactions with EFV are summarized in Table 5 [for pharmacokinetics data see Clinical Pharmacology (12.3, Tables 8 and 9)]. This table includes potentially significant interactions, but is not all inclusive.

Table 5. Established and Other Potentially Significant Drug Interactions with EFV: Alteration in Dose or Regimen May Be Recommended Based on Drug Interaction Studies or Predicted Interaction
Concomitant Drug; Class: Drug Name | Effect | Clinical Comment
Anticoagulant:; Warfarin | ↑ or ↓ warfarin | Monitor INR and adjust warfarin dosage if necessary.
Anticonvulsants:; Carbamazepine | ↓ carbamazepine [The interaction between EFV and the drug was evaluated in a clinical study. All other drug interactions shown are predicted.]; ↓ EFV | There are insufficient data to make a dose recommendation for EFV. Alternative anticonvulsant treatment should be used.
Phenytoin; Phenobarbital | ↓ anticonvulsant; ↓ EFV | Monitor anticonvulsant plasma levels periodically because of potential for reduction in anticonvulsant and/or EFV plasma levels.
Antidepressants:; Bupropion | ↓ bupropion | Increases in bupropion dosage should be guided by clinical response. Bupropion dose should not exceed the maximum recommended dose.
Sertraline | ↓ sertraline | Increases in sertraline dosage should be guided by clinical response.
Antifungals:; Itraconazole; Ketoconazole; Posaconazole | ↓ itraconazole; ↓ hydroxyitraconazole; ↓ ketoconazole; ↓ posaconazole | Consider alternative antifungal treatment because no dose recommendation for itraconazole or ketoconazole can be made.; Avoid concomitant use unless the benefit outweighs the risks.
Anti-infective:; Clarithromycin | ↓ clarithromycin; ↑ 14-OH metabolite | Consider alternatives to macrolide antibiotics because of the risk of QT interval prolongation.
Antimycobacterial:; Rifabutin; Rifampin | ↓ rifabutin; ↓ EFV | Increase daily dose of rifabutin by 50%. Consider doubling the rifabutin dose in regimens where rifabutin is given 2 or 3 times a week.; Increase EFV total daily dose to 800 mg once daily when coadministered with rifampin to patients weighing 50 kg or more.
Antimalarials:; Artemether/lumefantrine; Atovaquone/; proguanil | ↓ artemether; ↓ dihydroartemisinin; ↓ lumefantrine; ↓ atovaquone; ↓ proguanil | Consider alternatives to artemether/lumefantrine because of the risk of QT interval prolongation [see Warnings and Precautions (5.16)].; Concomitant administration is not recommended.
Calcium channel blockers:; Diltiazem; Others (e.g., felodipine,; nicardipine, nifedipine,; verapamil) | ↓diltiazem; ↓ desacetyl diltiazem; ↓ N-monodesmethyldiltiazem; ↓ calcium channel blocker | Diltiazem dose adjustments should be guided by clinical response (refer to the full prescribing information for diltiazem).; When coadministered with EFV, dosage adjustment of calcium channel blocker may be needed and should be guided by clinical response (refer to the full prescribing information for the calcium channel blocker).
HMG-CoA reductase inhibitors:; Atorvastatin; Pravastatin; Simvastatin | ↓ atorvastatin; ↓ pravastatin; ↓ simvastatin | Plasma concentrations of atorvastatin, pravastatin, and simvastatin decreased. Consult the full prescribing information for the HMG-CoA reductase inhibitor for guidance on individualizing the dose.
Hepatitis C antiviral agents:; Boceprevir; Elbasvir/Grazoprevir; Pibrentasvir/Glecaprevir; Simeprevir; Velpatasvir/Sofosbuvir; Velpatasvir/Sofosbuvir/ Voxilaprevir; Ledipasvir/Sofosbuvir | ↓ boceprevir; ↓ elbasvir; ↓ grazoprevir; ↓ pibrentasvir; ↓ glecaprevir; ↓ simeprevir; ↔ EFV; ↓ velpatasvir; ↓ velpatasvir; ↓ voxilaprevir; ↑ TDF | Concomitant administration of boceprevir is not recommended.; Coadministration of EFV with elbasvir/grazoprevir is contraindicated [see Contraindications (4)] because it may lead to loss of virologic response to elbasvir/grazoprevir.; Coadministration of EFV is not recommended because it may lead to reduced therapeutic effect of pibrentasvir/glecaprevir.; Concomitant administration of simeprevir is not recommended.; Coadministration of EFV and sofosbuvir/velpatasvir is not recommended because it may result in loss of therapeutic effect of sofosbuvir/velpatasvir.; Coadministration of EFV and sofosbuvir/velpatasvir/voxilaprevir is not recommended because it may result in loss of therapeutic effect of sofosbuvir/velpatasvir/voxilaprevir.; Monitor for adverse reactions associated with TDF.
Hepatitis B antiviral agents; Adefovir dipivoxil |  | Concomitant administration of adefovir dipivoxil is not recommended.
Hormonal contraceptives:; Oral Ethinyl estradiol/; Norgestimate; Implant Etonogestrel | ↓ active metabolites of norgestimate; ↓ etonogestrel | A reliable method of barrier contraception should be used in addition to hormonal contraceptives.; A reliable method of barrier contraception should be used in addition to hormonal contraceptives. Decreased exposure of etonogestrel may be expected. There have been postmarketing reports of contraceptive failure with etonogestrel in EFV-exposed patients.
Immunosuppressants:; Cyclosporine, tacrolimus,; sirolimus, and others metabolized by CYP3A | ↓ immunosuppressant | Dose adjustments of the immunosuppressant may be required. Close monitoring of immunosuppressant concentrations for at least 2 weeks (until stable concentrations are reached) is recommended when starting or stopping treatment with EFV.
Narcotic analgesic:; Methadone | ↓ methadone | Monitor for signs of methadone withdrawal and increase methadone dose if required to alleviate withdrawal symptoms.
This table is not all-inclusive.

7.6 Drugs without Clinically Significant Interactions

No dosage adjustment is recommended when SYMFI LO is administered with the following: aluminum/magnesium hydroxide antacids, azithromycin, cetirizine, famotidine, fluconazole, and lorazepam.

7.7 Drugs Inhibiting Organic Cation Transporters

3TC, a component of SYMFI LO, is predominantly eliminated in the urine by active organic cationic secretion. The possibility of interactions with other drugs administered concurrently should be considered, particularly when their main route of elimination is active renal secretion via the organic cationic transport system (e.g., trimethoprim) [see Clinical Pharmacology (12.3)]. No data are available regarding interactions with other drugs that have renal clearance mechanisms similar to that of 3TC.

7.8 Sorbitol

Coadministration of single doses of 3TC and sorbitol resulted in a sorbitol dose-dependent reduction in 3TC exposures. When possible, avoid use of sorbitol-containing medicines with 3TC [see Clinical Pharmacology (12.3)].

8 USE IN SPECIFIC POPULATIONS

8.1 Pregnancy

Pregnancy Exposure Registry

There is a pregnancy exposure registry that monitors pregnancy outcomes in women exposed to SYMFI LO during pregnancy. Healthcare providers are encouraged to register patients by calling the Antiretroviral Pregnancy Registry (APR) at 1-800-258-4263.

Risk Summary

There are retrospective case reports of neural tube defects in infants whose mothers were exposed to EFV-containing regimens in the first trimester of pregnancy.

Although a causal relationship has not been established between exposure to EFV in the first trimester and neural tube defects, similar malformations have been observed in studies conducted in monkeys at doses similar to the human dose. In addition, fetal and embryonic toxicities occurred in rats, at a dose ten times less than the human exposure at recommended clinical dose. Because of the potential risk of neural tube defects, EFV should not be used in the first trimester of pregnancy. Advise pregnant women of the potential risk to a fetus.

Prospective pregnancy data from the APR are not sufficient to adequately assess this risk of birth defects or miscarriage. EFV and 3TC have been evaluated in a limited number of women as reported to the APR. Available data from the APR show no difference in the risk of major birth defects for EFV and 3TC compared to the background rate for major birth defects of 2.7% in the U.S. reference population of the Metropolitan Atlanta Congenital Defects Program (MACDP). Available data from the APR also show no increase in the overall risk of major birth defects with first trimester exposure for TDF (2.1%) compared with the background rate for major birth defects of 2.7% in a U.S. reference population of the MACDP (see Data).

3TC produced embryonic toxicity in rabbits at a dose that produced similar human exposures as the recommended clinical dose. The relevance of animal findings to human pregnancy registry data is not known.

The rate of miscarriage is not reported in the APR. The estimated background rate of miscarriage in clinically recognized pregnancies in the U.S. general population is 15% to 20%. The background risk for major birth defects and miscarriage for the indicated population is unknown. The APR uses the MACDP as the U.S. reference population for birth defects in the general population. The MACDP evaluates women and infants from a limited geographic area and does not include outcomes for births that occurred at less than 20 weeks’ gestation.

Human Data

Efavirenz

There are retrospective postmarketing reports of findings consistent with neural tube defects, including meningomyelocele, all in infants of mothers exposed to EFV-containing regimens in the first trimester [see Warnings and Precautions (5.7)].

Based on prospective reports from the APR of approximately 1000 live births following exposure to EFV-containing regimens (including over 800 live births exposed in the first trimester), there was no difference between EFV and overall birth defects compared with the background birth defect rate of 2.7% in the U.S. reference population of the Metropolitan Atlanta Congenital Defects Program. As of the interim APR report issued December 2014, the prevalence of birth defects following first-trimester exposure was 2.3% (95% CI: 1.4%-3.6%). One of these prospectively reported defects with first-trimester exposure was a neural tube defect. A single case of anophthalmia with first-trimester exposure to EFV has also been prospectively reported. This case also included severe oblique facial clefts and amniotic banding, which have a known association with anophthalmia.

Lamivudine

Based on prospective reports from the APR of over 11,000 exposures to 3TC during pregnancy resulting in live births (including over 4,300 exposed in the first trimester), there was no difference between 3TC and overall risk of birth defects for 3TC compared with the background birth defect rate of 2.7% in the U.S. reference population of the MACDP. The prevalence of defects in live births was 3.1% (95% CI: 2.6% to 3.6%) following first trimester exposure to 3TC-containing regimens and 2.8% (95% CI: 2.5% to 3.3%) following second/third trimester exposure to 3TC-containing regimens.

3TC pharmacokinetics were studied in pregnant women during 2 clinical trials conducted in South Africa. The trials assessed pharmacokinetics in 16 women at 36 weeks’ gestation using 150 mg 3TC twice daily with zidovudine, 10 women at 38 weeks’ gestation using 150 mg 3TC twice daily with zidovudine, and 10 women at 38 weeks’ gestation using 3TC 300 mg twice daily without other antiretrovirals. These trials were not designed or powered to provide efficacy information.

3TC concentrations were generally similar in maternal, neonatal, and umbilical cord serum samples. In a subset of subjects, amniotic fluid specimens were collected following natural rupture of membranes and confirmed that 3TC crosses the placenta in humans. Based on limited data at delivery, median (range) amniotic fluid concentrations of 3TC were 3.9 (1.2 to 12.8)-fold greater compared with paired maternal serum concentration (n = 8).

Tenofovir Disoproxil Fumarate

Based on prospective reports from the APR exposures to TDF-containing regimens during pregnancy resulting in live births (including 3,342 exposed in the first trimester and 1,475 exposed in the second/third trimester), there was no increase in overall major birth defects with TDF compared with the background birth defect rate of 2.7% in a U.S. reference population of the MACDP. The prevalence of major birth defects in live births was 2.3% (95% CI: 1.8% to 2.8%) with first trimester exposure to TDF-containing regimens, and 2.1% (95% CI: 1.4% to 3.0%) with the second/third trimester exposure to TDF-containing regimens.

Prospective reports from the APR of overall major birth defects in pregnancies exposed to TDF are compared with a U.S. background major birth defect rate. Methodological limitations of the APR include the use of MACDP as the external comparator group. Limitations of using an external comparator include differences in methodology and populations, as well as confounding due to the underlying disease.

In published data from three controlled clinical trials, a total of 327 pregnant women with chronic HBV infection were administered tenofovir disoproxil fumarate from 28 to 32 weeks gestation through 1 to 2 months postpartum and followed for up to 12 months after delivery. There were no new safety findings in pregnant women compared with the known safety profile of tenofovir disoproxil fumarate in HBV-infected adults. An increased risk of adverse pregnancy-related outcomes was not observed; 2 stillbirths were identified, and there was 1 major birth defect (talipes) and 1 occurrence of multiple congenital abnormalities (not further specified) in tenofovir disoproxil fumarate-exposed infants. Infants were followed for up to 12 months after delivery; there were no clinically relevant drug-related safety findings in infants exposed to tenofovir disoproxil fumarate during late gestation.

Animal Data

Efavirenz

Effects of EFV on embryo-fetal development have been studied in three nonclinical species (cynomolgus monkeys, rats, and rabbits). In monkeys, EFV 60 mg/kg/day was administered to pregnant females throughout pregnancy (gestation days 20 through 150). The maternal systemic drug exposures (AUC) were 1.3 times the exposure in humans at the recommended clinical dose (600 mg/day), with fetal umbilical venous drug concentrations approximately 0.7 times the maternal values. Three of 20 fetuses/infants had one or more malformations; there were no malformed fetuses or infants from placebo-treated mothers. The malformations that occurred in these three monkey fetuses included anencephaly and unilateral anophthalmia in one fetus, microophthalmia in a second, and cleft palate in the third. There was no NOAEL (no observable adverse effect level) established for this study because only one dosage was evaluated. In rats, EFV was administered either during organogenesis (gestation days 7 to 18) or from gestation day 7 through lactation day 21 at 50, 100, or 200 mg/kg/day. Administration of 200 mg/kg/day in rats was associated with increase in the incidence of early resorptions; and doses 100 mg/kg/day and greater were associated with early neonatal mortality. The AUC at the NOAEL (50 mg/kg/day) in this rat study was 0.1 times that in humans at the recommended clinical dose. Drug concentrations in the milk on lactation day 10 were approximately 8 times higher than those in maternal plasma. In pregnant rabbits, EFV was neither embryo lethal nor teratogenic when administered at doses of 25, 50, and 75 mg/kg/day over the period of organogenesis (gestation days 6 through 18). The AUC at the NOAEL (75 mg/kg/day) in rabbits was 0.4 times that in humans at the recommended clinical dose.

Lamivudine

3TC was administered orally to pregnant rats (at 90, 600, and 4,000 mg per kg per day) and rabbits (at 90, 300, and 1,000 mg per kg per day and at 15, 40, and 90 mg per kg per day) during organogenesis (on gestation Days 7 through 16 [rat] and 8 through 20 [rabbit]). No evidence of fetal malformations due to 3TC was observed in rats and rabbits at doses producing plasma concentrations (Cmax) approximately 35 times higher than human exposure at the recommended daily dose. Evidence of early embryolethality was seen in the rabbit at system exposures (AUC) similar to those observed in humans, but there was no indication of this effect in the rat at plasma concentrations (Cmax) 35 times higher than human exposure at the recommended daily dose. Studies in pregnant rats showed that 3TC is transferred to the fetus through the placenta. In the fertility/pre- and postnatal development study in rats, 3TC was administered orally at doses of 180, 900, and 4,000 mg per kg per day (from prior to mating through postnatal Day 20). In the study, development of the offspring, including fertility and reproductive performance, was not affected by maternal administration of 3TC.

Tenofovir Disoproxil Fumarate

TDF was administered orally to pregnant rats (at 0, 50, 150, or 450 mg/kg/day) and rabbits (at 0, 30, 100, or 300 mg/kg/day) through organogenesis (on gestation days 7 through 17, and 6 through 18,respectively). No significant toxicological effects were observed in embryo-fetal toxicity studies performed with TDF in rats at doses up to 14 times the human dose based on body surface area comparisons and in rabbits at doses up to 19 times the human dose based on body surface area comparisons. In a pre/postnatal development study in rats, TDF was administered orally through lactation at doses up to 600 mg/kg/day; no adverse effects were observed in the offspring at tenofovir exposures of approximately 2.7 times higher than human exposures at the recommended daily dose of TDF.

8.2 Lactation

Risk Summary

The Centers for Disease Control and Prevention recommend that HIV-1-infected mothers not breastfeed their infants to avoid risking postnatal transmission of HIV-1 infection.

Efavirenz

EFV has been shown to pass into human breast milk. There is no information available on the effects of EFV on the breastfed infant, or the effects of EFV on milk production.

Lamivudine

3TC is present in human milk. Samples of breast milk obtained from 20 mothers receiving 3TC monotherapy, 300 mg twice daily (2 times the dose in SYMFI LO), had measurable concentrations of 3TC.There is no information on the effects of 3TC on the breastfed infant, or the effects of 3TC on milk production.

Tenofovir Disoproxil Fumarate

Based on published data, tenofovir has been shown to be present in human breast milk (see Data). It is not known if tenofovir affects milk production or has effects on the breastfed child.

Because of the potential for (1) HIV transmission (in HIV-negative infants); (2) developing viral resistance (in HIV-positive infants); and (3) adverse reactions in a breastfed infant similar to those seen in adults, instruct mothers not to breastfeed if they are receiving SYMFI LO.

Data

Tenofovir Disoproxil Fumarate

In a study of 50 HIV-uninfected, breastfeeding women on a tenofovir-containing regimen initiated between 1 and 24 weeks postpartum (median 13 weeks), tenofovir was undetectable in the plasma of most infants after 7 days of treatment in mothers. There were no serious adverse events in mothers or infants.

8.3 Females and Males of Reproductive Potential

Because of potential teratogenic effects, pregnancy should be avoided in women receiving SYMFI LO [see Warnings and Precautions (5.7), Use in Specific Populations (8.1)].

Pregnancy Testing

Females of reproductive potential should undergo pregnancy testing before initiation of SYMFI LO.

Contraception

Females of reproductive potential should use effective contraception during treatment with SYMFI LO and for 12 weeks after discontinuing SYMFI LO due to the long half-life of EFV. Barrier contraception should always be used in combination with other methods of contraception. Hormonal methods that contain progesterone may have decreased effectiveness [see Drug Interactions (7.5)].

8.4 Pediatric Use

The safety and effectiveness of SYMFI LO as a fixed-dose tablet in pediatric patients infected with HIV-1 and weighing at least 35 kg have been established based on clinical studies using the individual components (efavirenz, lamivudine, and tenofovir disoproxil fumarate).

8.5 Geriatric Use

Clinical studies of SYMFI LO did not include sufficient numbers of subjects aged 65 and over to determine whether they respond differently from younger subjects. In general, caution should be exercised in the administration of 3TC in elderly patients reflecting the greater frequency of decreased hepatic, renal, or cardiac function, and of concomitant disease or other drug therapy.

8.6 Renal Impairment

SYMFI LO is not recommended for patients with impaired renal function (i.e., creatinine clearance less than 50 mL/min) or patients with end-stage renal disease (ESRD) requiring hemodialysis because it is a fixed-dose combination formulation that cannot be adjusted [see Dosage and Administration (2.3)].

8.7 Hepatic Impairment

SYMFI LO is not recommended for patients with moderate or severe hepatic impairment because there are insufficient data to determine whether dose adjustment is necessary. Patients with mild hepatic impairment may be treated with SYMFI LO without any adjustment in dose [see Dosage and Administration (2.4), Warnings and Precautions (5.9) and Clinical Pharmacology (12.3)].

10 OVERDOSAGE

If overdose occurs, the patient must be monitored for evidence of toxicity, and standard supportive treatment applied as necessary.

Efavirenz: Some patients accidentally taking 600 mg twice daily have reported increased nervous system symptoms. One patient experienced involuntary muscle contractions.

Treatment of overdose with EFV should consist of general supportive measures, including monitoring of vital signs and observation of the patient’s clinical status. Administration of activated charcoal may be used to aid removal of unabsorbed drug. There is no specific antidote for overdose with efavirenz. Since efavirenz is highly protein bound, dialysis is unlikely to significantly remove the drug from blood.

Lamivudine: There is no known specific treatment for overdose with 3TC. If overdose occurs, the patient should be monitored and standard supportive treatment applied as required because a negligible amount of 3TC was removed via (4-hour) hemodialysis, continuous ambulatory peritoneal dialysis, and automated peritoneal dialysis, it is not known if continuous hemodialysis would provide clinical benefit in a 3TC overdose event.

Tenofovir Disoproxil Fumarate: Limited clinical experience at doses higher than the therapeutic dose of TDF 300 mg is available.

Tenofovir is efficiently removed by hemodialysis with an extraction coefficient of approximately 54%. Following a single 300 mg dose of tenofovir disoproxil fumarate, a 4-hour hemodialysis session removed approximately 10% of the administered tenofovir dose.

11 DESCRIPTION

SYMFI LO (efavirenz, lamivudine and tenofovir disoproxil fumarate) is a fixed-dose combination tablet for oral administration. Each tablet contains 400 mg of efavirenz, 300 mg of lamivudine and 300 mg of tenofovir disoproxil fumarate, which is equivalent to 245 mg of tenofovir disoproxil. Each tablet contains the following inactive ingredients: croscarmellose sodium, hydroxypropyl cellulose, lactose monohydrate, magnesium stearate, microcrystalline cellulose, polyethylene glycol, polyvinyl alcohol, sodium lauryl sulfate, talc, titanium dioxide and yellow iron oxide.

Efavirenz: Efavirenz (EFV) is an HIV-1 specific, non-nucleoside, reverse transcriptase inhibitor (NNRTI). Efavirenz is chemically described as (S)-6-Chloro-4-(cyclopropylethynyl)-1,4-dihydro-4-(trifluoromethyl)-2H-3,1-benzoxazin-2-one. Its molecular formula is C14H9ClF3NO2 and its structural formula is:

Efavirenz is a white to slightly pink crystalline powder with a molecular mass of 315.67. It is soluble in methanol and practically insoluble in water (< 10 microgram/mL).

Lamivudine: Lamivudine (also known as 3TC) is a synthetic nucleoside analogue with activity against HIV-1 and HBV. The chemical name of lamivudine is (-)-1-[(2R,5S)-2-(Hydroxymethyl)-1,3-oxathiolan-5-yl]cytosine. Lamivudine is the (-)enantiomer of a dideoxy analogue of cytidine. Lamivudine has also been referred to as (-)2′,3′-dideoxy, 3′-thiacytidine. It has a molecular formula of C8H11N3O3S and a molecular weight of 229.26 g per mol. It has the following structural formula:

Lamivudine is a white to off-white solid with a solubility of approximately 70 mg per mL in water at 20°C.

Tenofovir Disoproxil Fumarate: Tenofovir disoproxil fumarate (TDF) (a prodrug of tenofovir) is a fumaric acid salt of bis-isopropoxycarbonyloxymethyl ester derivative of tenofovir. TDF is converted in vivo to tenofovir, an acyclic nucleoside phosphonate (nucleotide) analog of adenosine 5’-monophosphate. Tenofovir exhibits activity against HIV-1 reverse transcriptase.

The chemical name of TDF is 9-[(R)-2-[[bis[[(isopropoxycarbonyl)oxy]methoxy]phosphinyl]methoxy]propyl]adenine fumarate (1:1). It has a molecular formula of C19H30N5O10P•C4H4O4 and a molecular weight of 635.51. It has the following structural formula:

Tenofovir disoproxil fumarate is a white to off-white powder that is freely soluble in dimethylformamide and soluble in methanol. It has an octanol/phosphate buffer (pH 6.5) partition coefficient (log p) of 1.25 at 25°C.

12 CLINICAL PHARMACOLOGY

12.1 Mechanism of Action

SYMFI LO is a fixed-dose combination of antiviral drugs EFV, 3TC, and TDF with antiviral activity against HIV-1 [see Microbiology (12.4)].

12.2 Pharmacodynamics

Cardiac Electrophysiology

The effect of EFV on the QTc interval was evaluated in an open-label, positive and placebo-controlled, fixed single sequence 3-period, 3-treatment crossover QT study in 58 healthy subjects enriched for CYP2B6 polymorphisms. The mean Cmax of EFV in subjects with CYP2B6 *6/*6 genotype following the administration of 600 mg daily dose for 14 days was 2.25-fold the mean Cmax observed in subjects with CYP2B6 *1/*1 genotype. A positive relationship between EFV concentration and QTc prolongation was observed. Based on the concentration-QTc relationship, the mean QTc prolongation and its upper bound 90% confidence interval are 8.7 ms and 11.3 ms in subjects with CYP2B6*6/*6 genotype following the administration of 600 mg daily dose for 14 days [see Warnings and Precautions (5.16)].

12.3 Pharmacokinetics

The effect of food on SYMFI LO has not been evaluated.

Efavirenz

In HIV-1-infected subjects, time-to-peak plasma concentrations were approximately 3 to 5 hours and steady-state plasma concentrations were reached in 6 to 10 days. EFV is highly bound (approximately 99.5 to 99.75%) to human plasma proteins, predominantly albumin. Following administration of ^14C-labeled EFV, 14 to 34% of the dose was recovered in the urine (mostly as metabolites) and 16 to 61% was recovered in feces (mostly as parent drug). In vitro studies suggest CYP3A and CYP2B6 are the major isozymes responsible for EFV metabolism. EFV has been shown to induce CYP enzymes, resulting in induction of its own metabolism. EFV has a terminal half-life of 52 to 76 hours after single doses and 40 to 55 hours after multiple doses.

Lamivudine

After oral administration of 2 mg/kg of 3TC twice a day to 9 adults with HIV-1, the peak serum 3TC concentration (Cmax) was 1.5 ± 0.5 mcg/mL (mean ± SD). The area under the plasma concentration versus time curve (AUC) and Cmax increased in proportion to oral dose over the range from 0.25 to 10 mg/kg and absolute bioavailability in 12 adult patients was 86% ± 16% (mean ± SD) for the 150-mg tablet and 87% ± 13% for the oral solution. Binding of 3TC to human plasma proteins is low (< 36%). Within 12 hours after a single oral dose of 3TC in 6 HIV-1-infected adults, 5.2% ± 1.4% (mean ± SD) of the dose was excreted as the trans-sulfoxide metabolite in the urine. The majority of 3TC is eliminated unchanged in urine by active organic cationic secretion and the observed mean elimination half-life (t1/2) ranged from 5 to 7 hours in most single-dose studies with serum sampling for 24 hours after dosing.

Tenofovir Disoproxil Fumarate

Following oral administration of a single 300 mg dose of TDF to HIV-1-infected subjects in the fasted state, maximum serum concentrations (Cmax) were achieved in 1.0 ± 0.4 hrs (mean ± SD) and Cmax and AUC values were 296 ± 90 ng/mL and 2287 ± 685 ng•hr/mL, respectively. The oral bioavailability of tenofovir from TDF in fasted subjects is approximately 25%. Less than 0.7% of tenofovir binds to human plasma proteins in vitro and the binding is independent of concentration over the range of 0.01 to 25 mcg/mL. Approximately 70 to 80% of the intravenous dose of tenofovir is recovered as unchanged drug in the urine. Tenofovir is eliminated by a combination of glomerular filtration and active tubular secretion with a renal clearance in adults with normal renal function of 243 ± 33 mL/min (mean ± SD). Following a single oral dose, the terminal elimination half-life of tenofovir is approximately 17 hours.

Special Populations

Race

Efavirenz and Lamivudine

There are no significant or clinically relevant racial differences in EFV and 3TC pharmacokinetics.

Tenofovir Disoproxil Fumarate

There were insufficient numbers from racial and ethnic groups other than Caucasian to adequately determine potential pharmacokinetic differences among these populations.

Gender

There are no significant or clinically relevant gender differences in the pharmacokinetics of EFV, 3TC, and TDF.

Geriatric Patients

The pharmacokinetics of 3TC and TDF have not been studied in patients over 65 years of age.

Patients with Renal Impairment

[See Use in Specific Populations (8.6).]

Efavirenz

The pharmacokinetics of EFV have not been studied in patients with renal impairment.

Lamivudine

The pharmacokinetics of 3TC are altered in subjects with renal impairment (Table 6).

Table 6. Pharmacokinetic Parameters (Mean ± SD) After a Single 300-mg Oral Dose of 3TC in Subjects with Varying Degrees of Renal Function
Parameter | Creatinine Clearance Criterion (Number of Subjects)
Parameter | > 60 mL/min; (n = 6) | 10-30 mL/min; (n = 4) | < 10 mL/min; (n = 6)
Creatinine clearance (mL/min) | 111 ± 14 | 28 ± 8 | 6 ± 2
Cmax (mcg/mL) | 2.6 ± 0.5 | 3.6 ± 0.8 | 5.8 ± 1.2
AUC∞ (mcg•h/mL) | 11.0 ± 1.7 | 48.0 ± 19 | 157 ± 74
Cl/F (mL/min) | 464 ± 76 | 114 ± 34 | 36 ± 11

Tenofovir Disoproxil Fumarate

The pharmacokinetics of TDF are altered in subjects with renal impairment [see Warnings and Precautions (5.4)]. In subjects with creatinine clearance below 50 mL/min or with end‑stage renal disease (ESRD) requiring dialysis, Cmax, and AUC0‑∞ of tenofovir were increased.

Table 7. Pharmacokinetic Parameters (Mean ± SD) of Tenofovir After a Single 300-mg Oral Dose of TDF in Subjects with Varying Degrees of Renal Function
Baseline Creatinine Clearance (mL/min) | > 80; (N = 3) | 50-80; (N = 10) | 30-49; (N = 8) | 12-29; (N = 11)
Cmax (μg/mL) | 0.34 ± 0.03 | 0.33 ± 0.06 | 0.37 ± 0.16 | 0.60 ± 0.19
AUC0-∞ (μg•hr/mL) | 2.18 ± 0.26 | 3.06 ± 0.93 | 6.01 ± 2.50 | 15.98 ± 7.22
CL/F(mL/min) | 1043.7 ± 115.4 | 807.7 ± 279.2 | 444.4 ± 209.8 | 177.0 ± 97.1
CLrenal (mL/min) | 243.5 ± 33.3 | 168.6 ± 27.5 | 100.6 ± 27.5 | 43.0 ± 31.2

Patients with Hepatic Impairment

Efavirenz

A multiple-dose study showed no significant effect on EFV pharmacokinetics in patients with mild hepatic impairment (Child-Pugh Class A) compared with controls. There were insufficient data to determine whether moderate or severe hepatic impairment (Child-Pugh Class B or C) affects EFV pharmacokinetics.

Lamivudine

The pharmacokinetic properties of 3TC have been determined in adults with impaired hepatic function. Pharmacokinetic parameters were not altered by diminishing hepatic function. Safety and efficacy of 3TC have not been established in the presence of decompensated liver disease.

Tenofovir Disoproxil Fumarate

The pharmacokinetics of tenofovir following a 300 mg single dose of TDF have been studied in non-HIV infected subjects with moderate to severe (Child-Pugh B to C) hepatic impairment. There were no substantial alterations in tenofovir pharmacokinetics in subjects with hepatic impairment compared with unimpaired subjects.

Assessment of Drug Interactions

[See Drug Interactions (7).]

Efavirenz

EFV has been shown in vivo to cause hepatic enzyme induction, thus increasing the biotransformation of some drugs metabolized by CYP3A and CYP2B6. In vitro studies have shown that EFV inhibited CYP isozymes 2C9, 2C19, and 3A4 with Ki values (8.5 to 17 µM) in the range of observed EFV plasma concentrations. In in vitro studies, EFV did not inhibit CYP2E1 and inhibited CYP2D6 and CYP1A2 (Ki values 82 to 160 µM) only at concentrations well above those achieved clinically. Coadministration of EFV with drugs primarily metabolized by 2C9, 2C19, and 3A isozymes may result in altered plasma concentrations of the coadministered drug. Drugs which induce CYP3A activity would be expected to increase the clearance of EFV resulting in lowered plasma concentrations.

Drug interaction studies were performed with EFV and other drugs likely to be coadministered or drugs commonly used as probes for pharmacokinetic interaction. The effects of coadministration of EFV on the Cmax, AUC, and Cmin are summarized in Table 8 (effect of EFV on other drugs) and Table 9 (effect of other drugs on EFV). For information regarding clinical recommendations see Drug Interactions (7.5).

Table 8. Effect of Efavirenz on Coadministered Drug Plasma Cmax, AUC, and Cmin
 |  |  | Number of Subjects | Coadministered Drug (mean % change)
Coadministered Drug | Dose | Efavirenz Dose | Number of Subjects | Cmax (90% CI) | AUC (90% CI) | Cmin (90% CI)
Boceprevir | 800 mg tid x 6 days | 600 mg qd x 16 days | NA | ↓ 8%; (↓ 22-↑ 8%) | ↓ 19%; (11-25%) | ↓ 44%; (26-58%)
Simeprevir | 150 mg qd x 14 days | 600 mg qd x 14 days | 23 | ↓ 51%; (↓ 46-↓ 56%) | ↓ 71%; (↓ 67-↓ 74%) | ↓ 91%; (↓ 88-↓ 92%)
Ledipasvir/; Sofosbuvir [Study conducted with ATRIPLA® coadministered with HARVONI®.] | 90/400 mg qd x 14 days | 600 mg qd x 14 days | 15 | ↓ 34; (↓ 25-↓ 41) | ↓ 34; (↓ 25-↓ 41) | ↓ 34; (↓ 24-↓ 43)
Ledipasvir |  |  |  | ↔ | ↔ | NA
Sofosbuvir; GS-331007 [The predominant circulating nucleoside metabolite of sofosbuvir.] |  |  |  | ↔ | ↔ | ↔
Sofosbuvir [Study conducted with ATRIPLA coadministered with SOVALDI® (sofosbuvir).] | 400 mg qd single dose | 600 mg qd x 14 days | 16 | ↓ 19; (↓ 40-↑ 10) | ↔ | NA
GS-331007 |  |  |  | ↓ 23; (↓ 16-↓ 30) | ↓ 16; (↓ 24-↓ 8) | NA
Sofosbuvir/; Velpatasvir [Study conducted with ATRIPLA coadministered with EPCLUSA®.] | 400/100 mg qd x 14 days | 600 mg qd x 14 days | 14
Sofosbuvir | 400/100 mg qd x 14 days | 600 mg qd x 14 days | 14 | ↑ 38; (↑ 14-↑ 67) | ↔ | NA
GS-331007 | 400/100 mg qd x 14 days | 600 mg qd x 14 days | 14 | ↓ 14; (↓ 20-↓ 7) | ↔ | ↔
Velpatasvir | 400/100 mg qd x 14 days | 600 mg qd x 14 days | 14 | ↓ 47; (↓ 57-↓ 36) | ↓ 53; (↓ 61-↓ 43) | ↓ 57; (↓ 64-↓ 48)
Azithromycin | 600 mg single dose | 400 mg qd x 7 days | 14 | ↑ 22%; (4-42%) | ↔ | NA
Clarithromycin | 500 mg q12h x 7 days | 400 mg qd x 7 days | 11 | ↓ 26%; (15-35%) | ↓ 39%; (30-46%) | ↓ 53%; (42-63%)
14-OH metabolite |  |  |  | ↑ 49%; (32-69%) | ↑ 34%; (18-53%) | ↑ 26%; (9-45%)
Fluconazole | 200 mg x 7 days | 400 mg qd x 7 days | 10 | ↔ | ↔ | ↔
Itraconazole | 200 mg q12h x 28 days | 600 mg qd x 14 days | 18 | ↓ 37%; (20-51%) | ↓ 39%; (21-53%) | ↓ 44%; (27-58%)
Hydroxy-itraconazole |  |  |  | ↓ 35%; (12-52%) | ↓ 37%; (14-55%) | ↓ 43%; (18-60%)
Posaconazole | 400 mg (oral suspension) bid x 10 and 20 days | 400 mg qd x 10 and 20 days | 11 | ↓ 45%; (34-53%) | ↓ 50%; (40-57%) | NA
Rifabutin | 300 mg qd x 14 days | 600 mg qd x 14 days | 9 | ↓ 32%; (15-46%) | ↓ 38%; (28-47%) | ↓ 45%; (31-56%)
Voriconazole | 400 mg po q12h x 1 day, then 200 mg po q12h x 8 days | 400 mg qd x 9 days | NA | ↓ 61% [90% CI not available.] | ↓ 77% | NA
 | 300 mg po q12h days 2‑7 | 300 mg qd x 7 days | NA | ↓ 36% [Relative to steady-state administration of voriconazole (400 mg for 1 day, then 200 mg po q12h for 2 days).]; (21-49%) | ↓ 55%; (45-62%) | NA
 | 400 mg po q12h days 2‑7 | 300 mg qd x 7 days | NA | ↑ 23%; (↓ 1-↑ 53%) | ↓ 7%; (↓ 23-↑ 13%) | NA
Artemether/; lumefantrine | Artemether 20 mg/ lumefantrine 120 mg tablets (6 4-tablet doses over 3 days) | 600 mg qd x 26 days | 12
Artemether | Artemether 20 mg/ lumefantrine 120 mg tablets (6 4-tablet doses over 3 days) | 600 mg qd x 26 days |  | ↓ 21% | ↓ 51% | NA
dihydroartemisinin | Artemether 20 mg/ lumefantrine 120 mg tablets (6 4-tablet doses over 3 days) | 600 mg qd x 26 days |  | ↓ 38% | ↓ 46% | NA
lumefantrine | Artemether 20 mg/ lumefantrine 120 mg tablets (6 4-tablet doses over 3 days) | 600 mg qd x 26 days |  | ↔ | ↓ 21% | NA
Atorvastatin | 10 mg qd x 4 days | 600 mg qd x 15 days | 14 | ↓ 14%; (1-26%) | ↓ 43%; (34-50%) | ↓ 69%; (49-81%)
Total active (including metabolites) |  |  |  | ↓ 15%; (2-26%) | ↓ 32%; (21-41%) | ↓ 48%; (23-64%)
Pravastatin | 40 mg qd x 4 days | 600 mg qd x 15 days | 13 | ↓ 32%; (↓ 59-↑ 12%) | ↓ 44%; (26-57%) | ↓ 19%; (0-35%)
Simvastatin | 40 mg qd x 4 days | 600 mg qd x 15 days | 14 | ↓ 72%; (63-79%) | ↓ 68%; (62-73%) | ↓ 45%; (20-62%)
Total active (including metabolites) | 40 mg qd x 4 days | 600 mg qd x 15 days | 14 | ↓ 68%; (55-78%) | ↓ 60%; (52-68%) | NA [Not available because of insufficient data.]
Carbamazepine | 200 mg qd x 3 days, 200 mg bid x 3 days, then 400 mg qd x 29 days | 600 mg qd x 14 days | 12 | ↓ 20%; (15-24%) | ↓ 27%; (20-33%) | ↓ 35%; (24-44%)
Epoxide metabolite |  |  |  | ↔ | ↔ | ↓ 13%; (↓ 30-↑ 7%)
Cetirizine | 10 mg single dose | 600 mg qd x 10 days | 11 | ↓ 24%; (18-30%) | ↔ | NA
Diltiazem | 240 mg x 21 days | 600 mg qd x 14 days | 13 | ↓ 60%; (50-68%) | ↓ 69%; (55-79%) | ↓ 63%; (44-75%)
Desacetyl diltiazem |  |  |  | ↓ 64%; (57-69%) | ↓ 75%; (59-84%) | ↓ 62%; (44-75%)
N-monodes-methyl diltiazem |  |  |  | ↓ 28%; (7-44%) | ↓ 37%; (17-52%) | ↓ 37%; (17-52%)
Ethinyl estradiol/ Norgestimate | 0.035 mg/0.25 mg x 14 days | 600 mg qd x 14 days
Ethinyl estradiol |  |  | 21 | ↔ | ↔ | ↔
Norelgestromine |  |  | 21 | ↓ 46%; (39-52%) | ↓ 64%; (62-67%) | ↓ 82%; (79-85%)
Levonorgestrel |  |  | 6 | ↓ 80%; (77-83%) | ↓ 83%; (79-87%) | ↓ 86%; (80-90%)
Lorazepam | 2 mg single dose | 600 mg qd x 10 days | 12 | ↑ 16%; (2-32%) | ↔ | NA
Methadone | Stable maintenance 35‑100 mg daily | 600 mg qd x 14‑21 days | 11 | ↓ 45%; (25-59%) | ↓ 52%; (33-66%) | NA
Bupropion | 150 mg single dose (sustained-release) | 600 mg qd x 14 days | 13 | ↓ 34%; (21-47%) | ↓ 55%; (48-62%) | NA
Hydroxy-bupropion |  |  |  | ↑ 50%; (20-80%) | ↔ | NA
Paroxetine | 20 mg qd x 14 days | 600 mg qd x 14 days | 16 | ↔ | ↔ | ↔
Sertraline | 50 mg qd x 14 days | 600 mg qd x 14 days | 13 | ↓ 29%; (15-40%) | ↓ 39%; (27-50%) | ↓ 46%; (31-58%)
↑ Indicates increase ↓ Indicates decrease ↔ Indicates no change or a mean increase or decrease of < 10%.
NA = not available.

Table 9. Effect of Coadministered Drug on Efavirenz Plasma Cmax, AUC, and Cmin
 |  |  | Number of Subjects | Efavirenz (mean % change)
Coadministered Drug | Dose | Efavirenz Dose | Number of Subjects | Cmax (90% CI) | AUC (90% CI) | Cmin (90% CI)
Boceprevir | 800 mg tid x 6 days | 600 mg qd x 16 days | NA | ↑ 11%; (2-20%) | ↑ 20%; (15-26%) | NA
Simeprevir | 150 mg qd x 14 days | 600 mg qd x 14 days | 23 | ↔ | ↓ 10%; (5-15%) | ↓ 13%; (7-19%)
Azithromycin | 600 mg single dose | 400 mg qd x 7 days | 14 | ↔ | ↔ | ↔
Clarithromycin | 500 mg q12h x 7 days | 400 mg qd x 7 days | 12 | ↑ 11%; (3-19%) | ↔ | ↔
Fluconazole | 200 mg x 7 days | 400 mg qd x 7 days | 10 | ↔ | ↑ 16%; (6-26%) | ↑ 22%; (5-41%)
Itraconazole | 200 mg q12h x 14 days | 600 mg qd x 28 days | 16 | ↔ | ↔ | ↔
Rifabutin | 300 mg qd x 14 days | 600 mg qd x 14 days | 11 | ↔ | ↔ | ↓ 12%; (↓ 24-↑ 1%)
Rifampin | 600 mg x 7 days | 600 mg qd x 7 days | 12 | ↓ 20%; (11-28%) | ↓ 26%; (15-36%) | ↓ 32%; (15-46%)
Voriconazole | 400 mg po q12h x 1 day, then 200 mg po q12h x 8 days | 400 mg qd x 9 days | NA | ↑ 38% [90% CI not available.] | ↑ 44% | NA
Voriconazole | 300 mg po q12h days 2-7 | 300 mg qd x 7 days | NA | ↓ 14% [Relative to steady-state administration of efavirenz (600 mg once daily for 9 days).]; (7-21%) | ↔ | NA
Voriconazole | 400 mg po q12h days 2-7 | 300 mg qd x 7 days | NA | ↔ | ↑ 17%; (6-29%) | NA
Artemether/; Lumefantrine | Artemether 20 mg/ lumefantrine 120 mg tablets (6 4-tablet doses over 3 days) | 600 mg qd x 26 days | 12 | ↔ | ↓ 17% | NA
Atorvastatin | 10 mg qd x 4 days | 600 mg qd x 15 days | 14 | ↔ | ↔ | ↔
Pravastatin | 40 mg qd x 4 days | 600 mg qd x 15 days | 11 | ↔ | ↔ | ↔
Simvastatin | 40 mg qd x 4 days | 600 mg qd x 15 days | 14 | ↓ 12%; (↓ 28-↑ 8%) | ↔ | ↓ 12%; (↓ 25-↑ 3%)
Aluminum hydroxide 400 mg, magnesium hydroxide 400 mg, plus simethicone 40 mg | 30 mL single dose | 400 mg single dose | 17 | ↔ | ↔ | NA
Carbamazepine | 200 mg qd x 3 days, 200 mg bid x 3 days, then 400 mg qd x 15 days | 600 mg qd x 35 days | 14 | ↓ 21%; (15-26%) | ↓ 36%; (32-40%) | ↓ 47%; (41-53%)
Cetirizine | 10 mg single dose | 600 mg qd x 10 days | 11 | ↔ | ↔ | ↔
Diltiazem | 240 mg x 14 days | 600 mg qd x 28 days | 12 | ↑ 16%; (6-26%) | ↑ 11%; (5-18%) | ↑ 13%; (1-26%)
Famotidine | 40 mg single dose | 400 mg single dose | 17 | ↔ | ↔ | NA
Paroxetine | 20 mg qd x 14 days | 600 mg qd x 14 days | 12 | ↔ | ↔ | ↔
Sertraline | 50 mg qd x 14 days | 600 mg qd x 14 days | 13 | ↑ 11%; (6-16%) | ↔ | ↔
↑ Indicates increase ↓ Indicates decrease ↔ Indicates no change or a mean increase or decrease of < 10%.
NA = not available.

Lamivudine

Effect of 3TC on the Pharmacokinetics of Other Agents

Based on in vitro study results, 3TC at therapeutic drug exposures is not expected to affect the pharmacokinetics of drugs that are substrates of the following transporters: organic anion transporter polypeptide 1B1/3 (OATP1B1/3), breast cancer resistance protein (BCRP), P-glycoprotein (P-gp), multidrug and toxin extrusion protein 1 (MATE1), MATE2-K, organic cation transporter 1 (OCT1), OCT2, or OCT3.

Effect of Other Agents on the Pharmacokinetics of 3TC

3TC is a substrate of MATE1, MATE2-K, and OCT2 in vitro. Trimethoprim (an inhibitor of these drug transporters) has been shown to increase 3TC plasma concentrations. This interaction is not considered clinically significant as no dose adjustment of 3TC is needed.

3TC is a substrate of P-gp and BCRP; however, considering its absolute bioavailability (87%), it is unlikely that these transporters play a significant role in the absorption of 3TC. Therefore, coadministration of drugs that are inhibitors of these efflux transporters is unlikely to affect the disposition and elimination of 3TC.

Interferon Alfa

There was no significant pharmacokinetic interaction between 3TC and interferon alfa in a trial of 19 healthy male subjects.

Ribavirin

In vitro data indicate ribavirin reduces phosphorylation of 3TC, stavudine, and zidovudine. However, no pharmacokinetic (e.g., plasma concentrations or intracellular triphosphorylated active metabolite concentrations) or pharmacodynamic (e.g., loss of HIV-1/HCV virologic suppression) interaction was observed when ribavirin and 3TC (n = 18), stavudine (n = 10), or zidovudine (n = 6) were coadministered as part of a multi-drug regimen to HIV-1/HCV co-infected subjects.

Sorbitol (Excipient)

3TC and sorbitol solutions were coadministered to 16 healthy adult subjects in an open-label, randomized-sequence, 4-period, crossover trial. Each subject received a single 300-mg dose of 3TC oral solution alone or coadministered with a single dose of 3.2 grams, 10.2 grams, or 13.4 grams of sorbitol in solution. Coadministration of 3TC with sorbitol resulted in dose-dependent decreases of 20%, 39%, and 44% in the AUC(0-24), 14%, 32%, and 36% in the AUC(∞), and 28%, 52%, and 55% in the Cmax of lamivudine, respectively.

Trimethoprim/Sulfamethoxazole

3TC and TMP/SMX were coadministered to 14 HIV-1-positive subjects in a single-center, open-label, randomized, crossover trial. Each subject received treatment with a single 300-mg dose of 3TC and TMP 160 mg/SMX 800 mg once a day for 5 days with concomitant administration of 3TC 300 mg with the fifth dose in a crossover design. Coadministration of TMP/SMX with 3TC resulted in an increase of 43% ± 23% (mean ± SD) in 3TC AUC∞, a decrease of 29% ± 13% in 3TC oral clearance, and a decrease of 30% ± 36% in 3TC renal clearance. The pharmacokinetic properties of TMP and SMX were not altered by coadministration with 3TC. There is no information regarding the effect on 3TC pharmacokinetics of higher doses of TMP/SMX such as those used in treating PCP.

Tenofovir Disoproxil Fumarate

At concentrations substantially higher (~300-fold) than those observed in vivo, tenofovir did not inhibit in vitro CYP3A4, CYP2D6, CYP2C9, or CYP2E1. However, a small (6%) but statistically significant reduction in metabolism of CYP1A substrate was observed. Based on the results of in vitro experiments and the known elimination pathway of tenofovir, the potential for CYP-mediated interactions involving TDF with other medicinal products is low.

Table 10 summarizes pharmacokinetic effects of coadministered drug on tenofovir pharmacokinetics. No clinically significant drug interactions have been observed between tenofovir and ribavirin.

Table 10. Drug Interactions: Changes in Pharmacokinetic Parameters for Tenofovir [Subjects received tenofovir disoproxil fumarate 300 mg once daily.] in the Presence of the Coadministered Drug
Coadministered Drug | Dose of Coadministered Drug (mg) | N | % Change of Tenofovir Pharmacokinetic Parameters [Increase = ↑; Decrease = ↓; No Effect = ↔; NC = Not Calculated]; (90% CI)
Coadministered Drug | Dose of Coadministered Drug (mg) | N | Cmax | AUC | Cmin
Ledipasvir/ Sofosbuvir [Data generated from simultaneous dosing with ledipasvir/sofosbuvir. Staggered administration (12 hours apart) provide similar results.] [Comparison based on exposures when administered as atazanavir/ritonavir + emtricitabine/tenofovir DF.] | 90/400 once daily x 10 days | 24 | ↑ 47; (↑ 37 to ↑ 58) | ↑ 35; (↑ 29 to ↑ 42) | ↑ 47; (↑ 38 to ↑ 57)
Ledipasvir/ Sofosbuvir [Comparison based on exposures when administered as darunavir/ritonavir + emtricitabine/tenofovir DF.] | 90/400 once daily x 10 days | 23 | ↑ 64; (↑ 54 to ↑ 74) | ↑ 50; (↑ 42 to ↑ 59) | ↑ 59; (↑ 49 to ↑ 70)
Ledipasvir/; Sofosbuvir [Study conducted with efavirenz/emtricitabine/tenofovir disoproxil fumarate coadministered with ledipasvir/sofosbuvir.] | 90/400 once daily x 14 days | 15 | ↑ 79; (↑ 56 to ↑ 104) | ↑ 98; (↑ 77 to ↑ 123) | ↑ 163; (↑ 132 to ↑ 197)
Sofosbuvir/ Velpatasvir [Study conducted with COMPLERA coadministered with EPCLUSA; coadministration with EPCLUSA also results in comparable increases in tenofovir exposures when TDF is administered as ATRIPLA, STRIBILD® (elvitegravir/cobicistat/FTC/TDF), TRUVADA + atazanavir/ritonavir, or TRUVADA + darunavir/ritonavir.] | 400/100 once daily | 24 | ↑ 44; (↑ 33 to ↑ 55) | ↑ 40; (↑ 34 to ↑ 46) | ↑ 84; (↑ 76 to ↑ 92)
Sofosbuvir/ Velpatasvir [Administered as raltegravir + FTC/TDF.] | 400/100 once daily | 30 | ↑ 46; (↑ 39 to ↑ 54) | ↑ 40; (↑ 34 to ↑ 45) | ↑ 70; (↑ 61 to ↑ 79)
Sofosbuvir/ Velpatasvir/ Voxilaprevir [Comparison based on exposures when administered as darunavir + ritonavir + FTC/TDF.] | 400/100/100 + Voxilaprevir [Study conducted with additional voxilaprevir 100 mg to achieve voxilaprevir exposures in HCV-infected patients.] 100 once daily | 29 | ↑ 48; (↑ 36 to ↑ 61) | ↑ 39; (↑ 32 to ↑ 46) | ↑ 47; (↑ 38 to ↑ 56)
Sofosbuvir [Study conducted with efavirenz/emtricitabine/tenofovir disoproxil fumarate coadministered with sofosbuvir.] | 400 single dose | 16 | ↑ 25; (↑ 8 to ↑ 45) | ↔ | ↔
Tacrolimus | 0.05 mg/kg twice daily x 7 days | 21 | ↑ 13; (↑ 1 to ↑ 27) | ↔ | ↔

12.4 Microbiology

Mechanism of Action

Efavirenz

EFV is an NNRTI of HIV-1. EFV activity is mediated predominantly by noncompetitive inhibition of HIV-1 reverse transcriptase (RT). HIV-2 RT and human cellular DNA polymerases α, β, γ, and δ are not inhibited by EFV.

Lamivudine

3TC is a synthetic nucleoside analogue with activity against HIV-1 and HBV. Intracellularly, 3TC is phosphorylated to its active 5’‑triphosphate metabolite, lamivudine triphosphate (3TC-TP). The principal mode of action of 3TC‑TP is inhibition of HIV-1 reverse transcriptase (RT) via DNA chain termination after incorporation of the nucleotide analogue.

Tenofovir Disoproxil Fumarate

TDF is an acyclic nucleoside phosphonate diester analog of adenosine monophosphate. TDF requires initial diester hydrolysis for conversion to tenofovir and subsequent phosphorylations by cellular enzymes to form tenofovir diphosphate (TDF-DP), an obligate chain terminator. Tenofovir diphosphate inhibits the activity of HIV-1 reverse transcriptase (RT) and HBV RT by competing with the natural substrate deoxyadenosine 5’-triphosphate and, after incorporation into DNA, by DNA chain termination. Tenofovir diphosphate is a weak inhibitor of mammalian DNA polymerases α, β, and mitochondrial DNA polymerase γ.

Antiviral Activity

Efavirenz

The concentration of EFV inhibiting replication of wild-type laboratory adapted strains and clinical isolates in cell culture by 90 to 95% (EC90 to 95) ranged from 1.7 to 25 nM in lymphoblastoid cell lines, peripheral blood mononuclear cells (PBMCs), and macrophage/monocyte cultures. EFV demonstrated antiviral activity against clade B and most non-clade B isolates (subtypes A, AE, AG, C, D, F, G, J, N), but had reduced antiviral activity against group O viruses.

Lamivudine

The antiviral activity of 3TC against HIV-1 was assessed in a number of cell lines (including monocytes and fresh human peripheral blood lymphocytes (PBMCs) using standard susceptibility assays. EC50 values were in the range of 3 to 15,000 nM. (1 μM = 0.23 mcg/mL). The median EC50 values of 3TC were 60 nM (range: 20 to 70 nM), 35 nM (range: 30 to 40 nM), 30 nM (range: 20 to 90 nM), 20 nM (range: 3 to 40 nM), 30 nM (range: 1 to 60 nM), 30 nM (range: 20 to 70 nM), 30 nM (range: 3 to 70 nM), and 30 nM (range: 20 to 90 nM) against HIV-1 clades A-G and group O viruses (n = 3 except n = 2 for clade B), respectively. The EC50 values against HIV-2 isolates (n = 4) ranged from 3 to 120 nM in PBMCs. 3TC was not antagonistic to all tested anti-HIV agents. Ribavirin (50 μM) used in the treatment of chronic HCV infection decreased the anti-HIV-1 activity of 3TC by 3.5-fold in MT-4 cells.

Tenofovir Disoproxil Fumarate

The antiviral activity of tenofovir against laboratory and clinical isolates of HIV-1 was assessed in lymphoblastoid cell lines, primary monocyte/macrophage cells and peripheral blood lymphocytes. The EC50 (50% effective concentration) values for tenofovir were in the range of 0.04 μM to 8.5 μM. Tenofovir displayed antiviral activity in cell culture against HIV-1 clades A, B, C, D, E, F, G, and O (EC50 values ranged from 0.5 μM to 2.2 μM) and strain-specific activity against HIV-2 (EC50 values ranged from 1.6 μM to 5.5 μM). Please see the full prescribing information for VIREAD® for information regarding the inhibitory activity of TDF against HBV.

Resistance

Efavirenz

In cell culture, HIV-1 isolates with reduced susceptibility to EFV (> 380-fold increase in EC90 value) emerged rapidly in the presence of drug. Genotypic characterization of these viruses identified single amino acid substitutions L100I or V179D, double substitutions L100I/V108I, and triple substitutions L100I/V179D/Y181C in reverse transcriptase.

Clinical isolates with reduced susceptibility in cell culture to EFV have been obtained. One or more RT substitutions at amino acid positions A98, L100, K101, K103, V106, V108, Y188, G190, P225, F227 and M230 were observed in patients failing treatment with EFV in combination with indinavir, or with 3TC plus zidovudine. The K103N substitution was the most frequently observed.

Lamivudine

3TC-resistant variants of HIV‑1 have been selected in cell culture. Genotypic analysis showed that resistance was predominantly due to a methionine to valine or isoleucine (M184V/I) substitution in reverse transcriptase.

Tenofovir Disoproxil Fumarate

HIV-1 isolates with reduced susceptibility to tenofovir have been selected in cell culture. These viruses expressed a K65R substitution in RT and showed a 2- to 4-fold reduction in susceptibility to tenofovir. In addition, a K70E substitution in HIV-1 RT has been selected by tenofovir and results in low-level reduced susceptibility to tenofovir. K65R substitutions developed in some subjects failing a tenofovir disoproxil fumarate regimen.

Cross-Resistance

Efavirenz

Cross-resistance among NNRTIs has been observed. Clinical isolates previously characterized as EFV-resistant were also phenotypically resistant in cell culture to delavirdine and nevirapine compared to baseline. Delavirdine- and/or nevirapine-resistant clinical viral isolates with NNRTI resistance-associated substitutions (A98G, L100I, K101E/P, K103N/S, V106A, Y181X, Y188X, G190X, P225H, F227L, or M230L) showed reduced susceptibility to EFV in cell culture. Greater than 90% of NRTI-resistant clinical isolates tested in cell culture retained susceptibility to EFV.

Lamivudine

Cross-resistance among NRTIs has been observed. 3TC-resistant HIV-1 isolates were cross-resistant in cell culture to didanosine (ddI). Cross-resistance is also expected with abacavir and emtricitabine as these select M184V substitutions.

Tenofovir Disoproxil Fumarate

Cross-resistance among certain HIV-1 NRTIs has been observed. The K65R and K70E substitutions selected by tenofovir are also selected in some HIV-1-infected subjects treated with abacavir or didanosine. HIV-1 isolates with the K65R substitution also showed reduced susceptibility to FTC and 3TC. HIV-1 isolates from subjects (N = 20) whose HIV-1 expressed a mean of 3 zidovudine-associated RT amino acid substitutions (M41L, D67N, K70R, L210W, T215Y/F, or K219Q/E/N) showed a 3.1-fold decrease in the susceptibility to tenofovir. Subjects whose virus expressed an L74V substitution without zidovudine resistance-associated substitutions (N = 8) had reduced response to VIREAD. Limited data are available for patients whose virus expressed a Y115F substitution (N = 3), Q151M substitution (N = 2), or T69 insertion (N = 4), all of whom had a reduced response.

13 NONCLINICAL TOXICOLOGY

13.1 Carcinogenesis, Mutagenesis, Impairment of Fertility

Efavirenz

Long-term carcinogenicity studies in mice and rats were carried out with efavirenz. Mice were dosed with 0, 25, 75, 150, or 300 mg/kg/day for 2 years. Incidences of hepatocellular adenomas and carcinomas and pulmonary alveolar/bronchiolar adenomas were increased above background in females. No increases in tumor incidence above background were seen in males. There was no NOAEL in female established for this study because tumor findings occurred at all doses. AUC at the NOAEL (150 mg/kg) in the males was approximately 0.9 times that in humans at the recommended clinical dose. In the rat study, no increases in tumor incidence were observed at doses up to 100 mg/kg/day, for which AUCs were 0.1 (males) or 0.2 (females) times those in humans at the recommended clinical dose.

EFV tested negative in a battery of in vitro and in vivo genotoxicity assays. These included bacterial mutation assays in S. typhimurium and E. coli, mammalian mutation assays in Chinese hamster ovary cells, chromosome aberration assays in human peripheral blood lymphocytes or Chinese hamster ovary cells, and an in vivo mouse bone marrow micronucleus assay.

EFV did not impair mating or fertility of male or female rats, and did not affect sperm of treated male rats. The reproductive performance of offspring born to female rats given EFV was not affected. The AUCs at the NOAEL values in male (200 mg/kg) and female (100 mg/kg) rats were approximately ≤ 0.15 times that in humans at the recommended clinical dose.

Lamivudine

Long-term carcinogenicity studies with 3TC in mice and rats showed no evidence of carcinogenic potential at exposures up to 10 times (mice) and 58 times (rats) the human exposures at the recommended dose of 300 mg. 3TC was not mutagenic in a microbial mutagenicity assay, in an in vitro cell transformation assay, in a rat micronucleus test, in a rat bone marrow cytogenetic assay, and in assay for unscheduled DNA synthesis in rat liver. 3TC showed no evidence of in vivo genotoxic activity in the rat at oral doses of up to 2000 mg per kg, producing plasma levels of 35 to 45 times those in humans at the recommended dose for HIV‑1 infection. In a study of reproductive performance, 3TC administered to rats at doses up to 4000 mg per kg per day, producing plasma levels 47 to 70 times those in humans, revealed no evidence of impaired fertility and no effect on the survival, growth, and development to weaning of the offspring.

Tenofovir Disoproxil Fumarate

Long-term oral carcinogenicity studies of TDF in mice and rats were carried out at exposures up to approximately 16 times (mice) and 5 times (rats) those observed in humans at the therapeutic dose for HIV-1 infection. At the high dose in female mice, liver adenomas were increased at exposures 16 times that in humans. In rats, the study was negative for carcinogenic findings at exposures up to 5 times that observed in humans at the therapeutic dose.

TDF was mutagenic in the in vitro mouse lymphoma assay and negative in an in vitro bacterial mutagenicity test (Ames test). In an in vivo mouse micronucleus assay, TDF was negative when administered to male mice.

There were no effects on fertility, mating performance or early embryonic development when TDF was administered to male rats at a dose equivalent to 10 times the human dose based on body surface area comparisons for 28 days prior to mating and to female rats for 15 days prior to mating through day seven of gestation. There was, however, an alteration of the estrous cycle in female rats.

13.2 Animal Toxicology and/or Pharmacology

Efavirenz

Nonsustained convulsions were observed in 6 of 20 monkeys receiving EFV at doses yielding plasma AUC values 4- to 13-fold greater than those in humans given the recommended dose [see Warnings and Precautions (5.11)].

Tenofovir Disoproxil Fumarate

Tenofovir and TDF administered in toxicology studies to rats, dogs, and monkeys at exposures (based on AUCs) greater than or equal to 6-fold those observed in humans caused bone toxicity. In monkeys the bone toxicity was diagnosed as osteomalacia. Osteomalacia observed in monkeys appeared to be reversible upon dose reduction or discontinuation of tenofovir. In rats and dogs, the bone toxicity manifested as reduced bone mineral density. The mechanism(s) underlying bone toxicity is unknown.

Evidence of renal toxicity was noted in 4 animal species. Increases in serum creatinine, BUN, glycosuria, proteinuria, phosphaturia, and/or calciuria and decreases in serum phosphate were observed to varying degrees in these animals. These toxicities were noted at exposures (based on AUCs) 2 to 20 times higher than those observed in humans. The relationship of the renal abnormalities, particularly the phosphaturia, to the bone toxicity is not known.

14 CLINICAL STUDIES

14.1 Clinical Efficacy in Patients with HIV-1 Infection

Treatment-Naïve Adult Patients

The efficacy of EFV 400 mg, 3TC 300 mg, and TDF 300 mg in the treatment of HIV-1 infection in adults with no antiretroviral treatment history was established in trials of:

- Trial 903 which evaluated the efficacy of a three-drug regimen including EFV 600 mg, 3TC 300 mg and TDF 300 mg
- ENCORE1, which evaluated the comparability of 400 mg of EFV in a triple drug regimen to a 600 mg dose of EFV in a triple drug regimen.

Trial 903

Data through 144 weeks are reported for Trial 903, a double-blind, active-controlled multicenter trial comparing EFV 600 mg + 3TC 300 mg + TDF 300 mg vs. EFV 600 mg + 3TC 300 mg + stavudine (d4T) 40 mg in 600 antiretroviral-naïve subjects. Subjects had a mean age of 36 years (range 18-64); 74% were male, 64% were Caucasian, and 20% were Black. The mean baseline CD4+ cell count was 279 cells/mm^3 (range 3-956) and median baseline plasma HIV-1 RNA was 77,600 copies/mL (range 417-5,130,000). Subjects were stratified by baseline HIV-1 RNA and CD4+ cell count. Forty-three percent of subjects had baseline viral loads > 100,000 copies/mL and 39% had CD4+ cell counts < 200 cells/mm^3. Table 11 provides treatment outcomes through 48 and 144 weeks.

Table 11. Outcomes of Randomized Treatment at Week 48 and 144 (Study 903)
Outcomes | At Week 48 |  | At Week 144
Outcomes | EFV + 3TC + TDF; (N = 299) | EFV + 3TC + d4T; (N = 301) | EFV + 3TC + TDF; (N = 299) | EFV + 3TC + d4T; (N = 301)
Responder [Subjects achieved and maintained confirmed HIV-1 RNA < 400 copies/mL through Week 48 and 144.] | 79% | 82% | 68% | 62%
Virologic failure [Includes confirmed viral rebound and failure to achieve confirmed < 400 copies/mL through Week 48 and 144.] | 6% | 4% | 10% | 8%
Rebound | 5% | 3% | 8% | 7%
Never suppressed | 0% | 1% | 0% | 0%
Added an antiretroviral agent | 1% | 1% | 2% | 1%
Death | < 1% | 1% | < 1% | 2%
Discontinued due to adverse event | 6% | 6% | 8% | 13%
Discontinued for other reasons [Includes lost to follow-up, subject’s withdrawal, noncompliance, protocol violation and other reasons.] | 8% | 7% | 14% | 15%

Achievement of plasma HIV-1 RNA concentrations of < 400 copies/mL at Week 144 was similar between the two treatment groups for the population stratified at baseline on the basis of HIV-1 RNA concentration (> or ≤ 100,000 copies/mL) and CD4+ cell count (< or ≥ 200 cells/mm^3). Through 144 weeks of therapy, 62% and 58% of subjects in the TDF and d4T arms, respectively, achieved and maintained confirmed HIV-1 RNA < 50 copies/mL. The mean increase from baseline in CD4+ cell count was 263 cells/mm^3 for the TDF arm and 283 cells/mm^3 for the d4T arm.

Through 144 weeks, 11 subjects in the TDF group and 9 subjects in the d4T group experienced a new CDC Class C event.

The ENCORE1 trial was a randomized, multinational clinical study comparing EFV 400 mg vs. EFV 600 mg in 630 antiretroviral-naïve adult subjects. Subjects were randomized 1:1 to receive EFV 400 mg in combination with TDF 300 mg plus FTC 200 mg all given once daily or EFV 600 mg in combination with TDF 300 mg/FTC 200 mg given once daily. The randomization was stratified by the clinical sites and the screening visit plasma HIV RNA level, either < 100,000 copies/mL or ≥ 100,000 copies/mL.

Subjects had a mean age of 36 years (range 18 to 69), 68% were male, 37% were of African heritage, 33% were of Asian ethnicity, 17% were Hispanic and 13% were Caucasian.

The mean baseline CD4+ cell count was 273 cells/mm^3 (range 38 to 679). Median baseline viral load was 56,469 copies/mL (range 162 to 10,000,000). Thirty-four percent of subjects had baseline viral load of ≥ 100,000 copies/mL.

Treatment outcomes through Week 48 are presented in Table 12.

Table 12. Virologic Outcomes of Randomized Treatment in Trial ENCORE1 in Treatment-Naïve Subjects at Week 48
 | At Week 48
Outcomes (< 50 copies/mL) | EFV 400 mg + FTC + TDF; (N = 321) | EFV 600 mg + FTC + TDF; (N = 309)
Responder [Subjects achieved confirmed HIV-1 RNA < 50 copies/mL at Week 48.]; HIV-1 RNA < 50 copies/mL | 86% | 84%
Virologic failure [Includes confirmed viral rebound and failure to achieve confirmed < 50 copies/mL through Week 48.]; HIV-1 RNA ≥ 50 copies/mL | 11% | 11%
Rebound | 9% | 8%
Never suppressed | 2% | 3%
Death | 1% | 1%
Discontinued for other reasons [Includes discontinued due to Adverse Event, lost to follow-up, subject’s withdrawal, noncompliance, protocol violation and other reasons.] | 2% | 4%

Achievement of plasma HIV-1 RNA concentrations of less than 50 copies/mL at Week 48 was similar between the two treatment groups for the population stratified at baseline on the basis of HIV-1 RNA concentration (< or ≥ 100,000 copies/mL). The mean increase at Week 48 from baseline in CD4^+ cell count was 183 cells/mm^3 for the EFV 400 mg arm and 158 cells/mm^3 for the EFV 600 mg arm. Through 48 weeks, 11 subjects in the EFV 400 mg group and 5 subjects in the EFV 600 mg group experienced a new CDC Class C event.

16 HOW SUPPLIED/STORAGE AND HANDLING

SYMFI LO tablets are supplied as fixed-dosed combination tablets containing 400 mg of efavirenz, 300 mg of lamivudine, and 300 mg of tenofovir disoproxil fumarate equivalent to 245 mg of tenofovir disoproxil. SYMFI LO tablets are white to off-white, film-coated, oval tablets debossed with “M” on one side and “TLE” on the other side.

They are supplied as:

NDC 49502-425-93
unit of use cartons containing bottles of 30 tablets with desiccant, induction seal, and child-resistant cap.

NDC 49502-425-77
unit of use cartons containing bottles of 90 tablets with desiccant, induction seal, and child-resistant cap.

Store below 30°C (86°F).

Dispense in original container.

17 PATIENT COUNSELING INFORMATION

Advise the patient to read the FDA-approved patient labeling (Patient Information).

Drug Interactions: SYMFI LO may interact with many drugs; therefore, advise patients to report to their healthcare provider the use of any other prescription, nonprescription medication, or herbal products, particularly St. John’s wort [see Contraindications (4) and Drug Interactions (7)].

Post Treatment Acute Exacerbation of Hepatitis B in Patients with HBV Co-Infection: Inform patients that severe acute exacerbations of hepatitis have been reported in patients who are infected with HBV or coinfected with HBV and HIV-1 and have discontinued 3TC and TDF, components of SYMFI LO. Test patients with HIV-1 for hepatitis B virus (HBV) before initiating antiretroviral therapy. In patients with chronic hepatitis B, it is important to obtain HIV antibody testing prior to initiating 3TC and TDF, components of SYMFI LO [see Warnings and Precautions (5.1)].

Lactic Acidosis and Severe Hepatomegaly: Inform patients that lactic acidosis and severe hepatomegaly with steatosis, including fatal cases, have been reported. Treatment with SYMFI LO should be suspended in any patient who develops clinical symptoms suggestive of lactic acidosis or pronounced hepatotoxicity (including nausea, vomiting, unusual or unexpected stomach discomfort, and weakness) [see Warnings and Precautions (5.2)].

New Onset or Worsening Renal Impairment: Inform patients that renal impairment, including cases of acute renal failure and Fanconi syndrome, has been reported. Advise patients with impaired renal function (i.e., creatinine clearance less than 50 mL/min) or patients with end-stage renal disease (ESRD) requiring hemodialysis to avoid SYMFI LO with concurrent or recent use of a nephrotoxic agent (e.g., high-dose or multiple NSAIDs) for patients [see Dosage and Administration (2.3), Warnings and Precautions (5.4)].

Psychiatric Symptoms: Inform patients that serious psychiatric symptoms including severe depression, suicide attempts, aggressive behavior, delusions, paranoia, psychosis-like symptoms and catatonia have been reported in patients receiving EFV [see Warnings and Precautions (5.5)]. Advise patients to seek immediate medical evaluation if they experience severe psychiatric adverse experiences. Advise patients to inform their physician of any history of mental illness or substance abuse.

Nervous System Symptoms: Inform patients that central nervous system symptoms (NSS) including dizziness, insomnia, impaired concentration, drowsiness, and abnormal dreams are commonly reported during the first weeks of therapy with EFV, a component of SYMFI LO [see Warnings and Precautions (5.6)]. Dosing at bedtime may improve the tolerability of these symptoms, which are likely to improve with continued therapy. Alert patients to the potential for additive effects when used concomitantly with alcohol or psychoactive drugs. Instruct patients that if they experience NSS they should avoid potentially hazardous tasks such as driving or operating machinery.

Inform patients that there is a risk of developing late-onset neurotoxicity, including ataxia and encephalopathy, which may occur months to years after beginning efavirenz therapy [see Warnings and Precautions (5.6)].

Embryo-Fetal Toxicity: Advise female patients that EFV, a component of SYMFI LO may cause fetal harm when administered during the first trimester to a pregnant woman. Advise females of reproductive potential to use effective contraception as well as a barrier method during treatment with SYMFI LO and for 12 weeks after discontinuation of use. Advise patients to contact their healthcare provider if they plan to become pregnant, become pregnant, or if pregnancy is suspected during treatment with SYMFI LO [see Warnings and Precautions (5.7), Use in Specific Populations (8.1, 8.3)].

Rash: Inform patients that rash is a common side effect of EFV [see Warnings and Precautions (5.8)]. Rashes usually go away without any change in treatment. However, since rash may be serious, patients should be advised to contact their physician promptly if rash occurs.

Hepatotoxicity: Inform patients to watch for early warning signs of liver inflammation or failure, such as fatigue, weakness, lack of appetite, nausea and vomiting, as well as later signs such as jaundice, confusion, abdominal swelling, and discolored feces and to consult their healthcare provider promptly if such symptoms occur [see Warnings and Precautions (5.9)].

Pancreatitis: Advise patients or guardians to monitor pediatric patients for signs and symptoms of pancreatitis [see Warnings and Precautions (5.10)].

Convulsions: Advise patients that convulsions have been observed in patients receiving EFV, a component of SYMFI LO, generally in patients with known medical history of seizures [see Warnings and Precautions (5.11)].

Lipid Elevations: Advise patients treatment with EFV, a component of SYMFI LO has resulted in increases in the concentration of total cholesterol and triglycerides [see Warnings and Precautions (5.12)].

Bone Loss and Mineralization Effects: Inform patients that decreases in bone mineral density have been observed with the use of 3TC and TDF, components of SYMFI LO, in patients with HIV [see Warnings and Precautions (5.13)].

Immune Reconstitution Syndrome: Advise patients to inform their healthcare provider immediately of any symptoms of infection, as in some patients with advanced HIV infection, signs and symptoms of inflammation from previous infections may occur soon after anti-HIV treatment is started [see Warnings and Precautions (5.14)].

Fat Redistribution: Inform patients that redistribution or accumulation of body fat may occur in patients receiving antiretroviral therapy, including SYMFI LO, and that the cause and long‑term health effects of these conditions are not known at this time [see Warnings and Precautions (5.15)].

Administration Instructions: Inform patients that it is important to take SYMFI LO once daily on a regular dosing schedule on an empty stomach, preferably at bedtime, and to avoid missing doses as it can result in development of resistance. Advise patients if a dose is missed, take it as soon as possible unless it is almost time for the next dose. Also advise patients that dosing at bedtime may improve the tolerability of nervous system symptoms [see Dosage and Administration (2.2)].

Pregnancy Registry: Advise patients that there is an antiretroviral pregnancy registry to monitor fetal outcomes in women exposed to SYMFI LO [see Use in Specific Populations (8.1)].

Lactation: Instruct women with HIV-1 infection not to breastfeed because HIV-1 can be passed to the baby in breast milk [see Use in Specific Populations (8.2)].

SYMFI LO® is a registered trademark of Mylan Pharmaceuticals Inc.

Other brands listed are the registered trademarks of their respective owners and are not trademarks of Mylan Pharmaceuticals Inc.

Rx only

Manufactured for:
Mylan Specialty L.P.
Morgantown, WV 26505 U.S.A.

Manufactured by:
Mylan Laboratories Limited
Hyderabad — 500 096, India

Patient Information

SYMFI LO® (SIM-fee LOW)

(efavirenz, lamivudine and tenofovir disoproxil fumarate)

tablets

What is the most important information I should know about SYMFI LO?

SYMFI LO can cause serious side effects, including:

- Worsening of Hepatitis B virus infection. If you have Human Immunodeficiency Virus type 1 (HIV-1) and Hepatitis B Virus (HBV) infection, your HBV may get worse (flare-up) if you stop taking SYMFI LO. A “flare-up” is when your HBV infection suddenly returns in a worse way than before. Your healthcare provider will test you for HBV infection before you start treatment with SYMFI LO.
  - It is not known if SYMFI LO is safe and effective in people who have both HIV-1 and HBV infection.
  - Do not run out of SYMFI LO. Refill your prescription or talk to your healthcare provider before your SYMFI LO is all gone.
  - Do not stop SYMFI LO without first talking to your healthcare provider. If you stop taking SYMFI LO, your healthcare provider will need to check your health often and do blood tests regularly for several months to check your liver.

For more information about side effects, see “What are the possible side effects of SYMFI LO?”

What is SYMFI LO?

SYMFI LO is a prescription medicine that is used without other antiretroviral medicines to treat Human Immunodeficiency Virus-1 (HIV-1) in people weighing at least 35 kg.

HIV-1 is the virus that causes AIDS (Acquired Immune Deficiency Syndrome).

SYMFI LO contains the prescription medicines efavirenz, lamivudine and tenofovir disoproxil fumarate.

SYMFI LO is not for use in children weighing less than 35 kg.

Do not take SYMFI LO if you:

- are allergic to efavirenz, lamivudine, tenofovir disoproxil fumarate, or any of the ingredients in SYMFI LO. See the end of this Patient Information leaflet for a complete list of ingredients in SYMFI LO.
- are currently taking elbasvir and grazoprevir.

Before you take SYMFI LO, tell your healthcare provider about all of your medical conditions, including if you:

- have liver problems, including hepatitis B or C infection
- have kidney problems, including end-stage renal disease (ESRD) that requires dialysis
- have a history of mental health problems
- have a history of drug or alcohol abuse
- have a heart problem, including QT prolongation
- have bone problems, including a history of bone fractures
- have a history of seizures
- are pregnant or plan to become pregnant. SYMFI LO may harm your unborn baby.
  - You should not become pregnant during treatment with SYMFI LO. Tell your healthcare provider right away if you think you may be pregnant or become pregnant during treatment with SYMFI LO.
  - Females who are able to become pregnant should use effective birth control during treatment with SYMFI LO and for 12 weeks after stopping treatment. A barrier form of birth control should always be used along with another type of birth control.
  - If you are able to become pregnant, your healthcare provider should do a pregnancy test before you start SYMFI LO.
Pregnancy Registry. There is a pregnancy registry for women who take SYMFI LO during pregnancy. The purpose of this registry is to collect information about the health of you and your baby. Talk to your healthcare provider about how you can take part in this registry.
- are breastfeeding or plan to breastfeed. Do not breastfeed if you take SYMFI LO.
  - You should not breastfeed if you have HIV-1 because of the risk of passing HIV-1 to your baby.
  - Talk to your healthcare provider about the best way to feed your baby.

Tell your healthcare provider about all the medicines you take, including prescription and over-the-counter medicines, vitamins and herbal supplements.

Some medicines interact with SYMFI LO. SYMFI LO may affect the way other medicines work, and other medicines may affect how SYMFI LO works. Keep a list of your medicines and show it to your healthcare provider and pharmacist when you get a new medicine.

- You can ask your healthcare provider or pharmacist for a list of medicines that interact with SYMFI LO.
- Do not start taking a new medicine without telling your healthcare provider. Your healthcare provider can tell you if it is safe to take SYMFI LO with other medicines.

How should I take SYMFI LO?

- Take SYMFI LO exactly as your healthcare provider tells you to take it.
- Take SYMFI LO 1 time each day, preferably at bedtime. Taking SYMFI LO at bedtime might help to make some of the side effects less bothersome.
- Take SYMFI LO on an empty stomach.
- Do not miss a dose of SYMFI LO. If you miss a dose, take the missed dose as soon as you remember. If it is almost time for your next dose of SYMFI LO, do not take the missed dose. Take the next dose at your regular time.
- Stay under the care of your healthcare provider during treatment with SYMFI LO.
- Do not run out of SYMFI LO. The virus in your blood may increase and the virus may become harder to treat. When your supply starts to run low, get more from your healthcare provider or pharmacy.
- If you take too much SYMFI LO, go to the nearest hospital emergency room right away.

What should I avoid while taking SYMFI LO?

You should avoid taking medicines that contain sorbitol during treatment with SYMFI LO.

What are the possible side effects of SYMFI LO?

SYMFI LO may cause serious side effects, including:

- See “What is the most important information I should know about SYMFI LO?”
- Build-up of an acid in your blood (lactic acidosis). Lactic acidosis can happen in some people who take SYMFI LO. Lactic acidosis is a serious medical emergency that can lead to death. Call your healthcare provider right away if you get any of the following symptoms that could be signs of lactic acidosis:

- feel very weak or tired
- unusual (not normal) muscle pain
- trouble breathing
- stomach pain with nausea or vomiting

- feel cold, especially in your arms and legs
- feel dizzy or lightheaded
- have a fast or irregular heartbeat

- Severe liver problems can happen in people who take SYMFI LO. In some cases, these severe liver problems can lead to death. Your liver may become large (hepatomegaly) and you may develop fat in your liver (steatosis). Inflammation of your liver (hepatitis) that can lead to liver failure requiring a liver transplant has been reported in some people treated with SYMFI LO. Your healthcare provider may do blood tests to check your liver before and during treatment with SYMFI LO.
  Call your healthcare provider right away if you get any of the following signs or symptoms of liver problems:

- your skin or the white part of your eyes turns yellow (jaundice)
- dark or “tea-colored” urine
- light-colored stools (bowel movements)
- confusion
- tiredness

- loss of appetite for several days or longer
- nausea and vomiting
- pain, aching, or tenderness on the right side of your stomach-area
- weakness
- stomach (abdomen) swelling

You may be more likely to get lactic acidosis or serious liver problems if you are female or very overweight (obese).
2. New or worse kidney problems, including kidney failure. Your healthcare provider may do blood and urine tests to check your kidneys before and during treatment with SYMFI LO. Tell your healthcare provider if you get signs and symptoms of kidney problems, including bone pain that does not go away or worsening bone pain, pain in your arms, hands, legs or feet, broken (fractured) bones, muscle pain or weakness.
3. Serious mental health problems. Get medical help right away if you get any of the following symptoms:

- feel sad or hopeless
- feel anxious or restless
- do not trust other people
- hear or see things that are not real

- are not able to move or speak normally
- have thoughts of hurting yourself (suicide) or have tried to hurt yourself or others
- are not able to tell the difference between what is true or real and what is false or unreal

- Nervous system symptoms are common in people who take SYMFI LO and can be severe. These symptoms usually begin during the first or second day of treatment with SYMFI LO and usually go away after 2 to 4 weeks of treatment. Some symptoms may occur months to years after beginning SYMFI LO therapy. These symptoms may become worse if you drink alcohol, take a medicine for mental health problems, or use certain street drugs during treatment with SYMFI LO. Symptoms may include:

- dizziness
- trouble sleeping
- unusual dreams

- trouble concentrating
- drowsiness
- lack of coordination or balance

If you have dizziness, trouble concentrating or drowsiness, do not drive a car, use machinery, or do anything that needs you to be alert.
Some nervous system symptoms (e.g., confusion, slow thoughts and physical movement, and delusions [false beliefs] or hallucinations [seeing or hearing things that others do not see or hear]) may occur months to years after beginning SYMFI LO therapy. Promptly contact your health care provider should any of these symptoms occur.
3. Skin reactions and allergic reactions. Skin reactions or rash can happen and can sometimes be severe. Skin rash usually goes away without any change in treatment. If you develop a rash or a rash with any of the following symptoms, call your healthcare provider right away:

- itching
- fever
- swelling of your face
- blisters or skin lesions

- peeling skin
- mouth sores
- red or inflamed eyes

- Risk of inflammation of the pancreas (pancreatitis). Children may be at risk for developing pancreatitis during treatment with SYMFI LO if they:
  - have taken nucleoside analogue medicines in the past
  - have a history of pancreatitis
  - have other risk factors for pancreatitis
Call your healthcare provider right away if your child develops signs and symptoms of pancreatitis including severe upper stomach-area pain, with or without nausea and vomiting. Your healthcare provider may tell you to stop giving SYMFI LO to your child if their symptoms and blood test results show that your child may have pancreatitis.
- Seizures. Seizures are more likely to happen if you have had seizures in the past.
- Increases in blood fat levels (cholesterol and triglycerides). Your healthcare provider will check your blood fat levels before and during treatment with SYMFI LO.
- Bone problems can happen in some people who take SYMFI LO. Bone problems include bone pain, softening or thinning (which may lead to fractures). Your healthcare provider may need to do tests to check your bones. Tell your healthcare provider if you have any bone pain, pain in your hands or feet, or muscle pain or weakness during treatment with SYMFI LO.
- Changes in your immune system (Immune Reconstitution Syndrome) can happen when you start taking HIV-1 medicines. Your immune system may get stronger and begin to fight infections that have been hidden in your body for a long time. Tell your healthcare provider if you start having new symptoms after starting your HIV-1 medicine.
- Changes in body fat can happen in some people who take HIV-1 medicines. These changes may include increased amount of fat in the upper back and neck (“buffalo hump”), breast, and around the main part of your body (trunk). Loss of fat from the legs, arms, and face may also happen. The cause and long-term health effects of these conditions are not known.
- Changes in the electrical activity of your heart called QT prolongation. QT prolongation can cause irregular heartbeats that can be life-threatening. Tell your healthcare provider if you feel faint, lightheaded, dizzy, or feel your heart beating irregularly or fast during treatment with SYMFI LO.

The most common side effects of SYMFI LO are rash and dizziness.

Tell your healthcare provider if you have any side effect that bothers you or that does not go away.

These are not all the possible side effects of SYMFI LO. Call your doctor for medical advice about side effects. You may report side effects to FDA at 1-800-FDA-1088.

How should I store SYMFI LO?

- Store SYMFI LO tablets below 86°F (30°C).
- Keep SYMFI LO tablets in the original container.

Keep SYMFI LO and all medicines out of the reach of children.

General information about the safe and effective use of SYMFI LO.

Medicines are sometimes prescribed for purposes other than those listed in a Patient Information leaflet. Do not use SYMFI LO for a condition for which it was not prescribed. Do not give SYMFI LO to other people, even if they have the same symptoms that you have. It may harm them. If you would like more information, talk with your healthcare provider. You can ask your pharmacist or healthcare provider for information about SYMFI LO that is written for health professionals.

What are the ingredients in SYMFI LO?

Active ingredient: efavirenz, lamivudine, and tenofovir disoproxil fumarate

Inactive ingredients: croscarmellose sodium, hydroxypropyl cellulose, lactose monohydrate, magnesium stearate, microcrystalline cellulose, polyethylene glycol, polyvinyl alcohol, sodium lauryl sulfate, talc, titanium dioxide and yellow iron oxide.

SYMFI LO® is a registered trademark of Mylan Pharmaceuticals Inc.

Other brands listed are the registered trademarks of their respective owners and are not trademarks of Mylan Pharmaceuticals Inc.

Manufactured for:
Mylan Specialty L.P.
Morgantown, WV 26505 U.S.A.

Manufactured by:
Mylan Laboratories Limited
Hyderabad — 500 096, India

75074360

MS:ELTDF:R2

For more information, call Mylan at 1-877-446-3679 (1-877-4-INFO-RX).

This Patient Information has been approved by the U.S. Food and Drug Administration. Revised: 10/2019

PRINCIPAL DISPLAY PANEL – 400 mg/300 mg/300 mg

NDC 49502-425-93 Rx only

SYMFI LO®
(efavirenz, lamivudine,
and tenofovir disoproxil
fumarate) tablets
400 mg/300 mg/300 mg*

Note to pharmacist: Do not cover
ALERT box with pharmacy label.

ALERT: Find out about
medicines that should NOT
be taken with SYMFI LO®.

30 tablets

*Each film-coated tablet contains:
Efavirenz, USP 400 mg
Lamivudine, USP 300 mg
Tenofovir Disoproxil Fumarate 300 mg
(equivalent to 245 mg of tenofovir
disoproxil)

Usual Dosage: See accompanying
prescribing information.

Keep this and all medication
out of the reach of children.

Store below 30°C (86°F).

Dispense only in original container.

Keep container tightly closed.

Manufactured for:
Mylan Specialty L.P.
Morgantown, WV 26505 U.S.A.

Made in India

Code No.: MP/DRUGS/25/1/2014

MS:MXI:42593:1C:R2

SYMFI LO® is a registered trademark of Mylan Pharmaceuticals Inc.